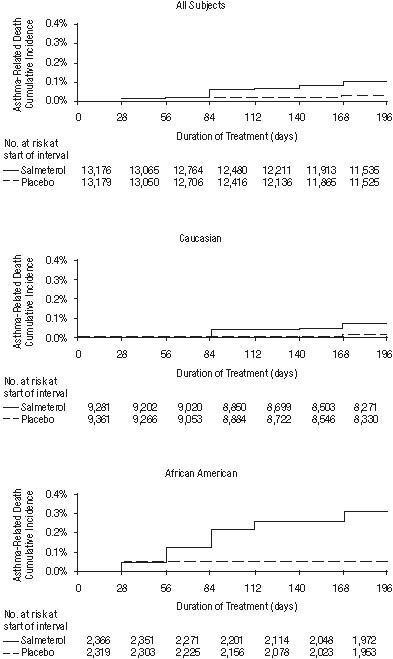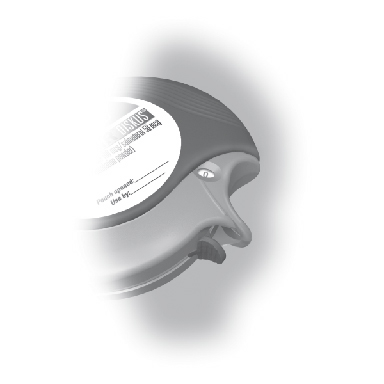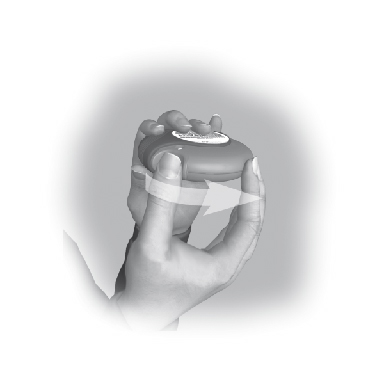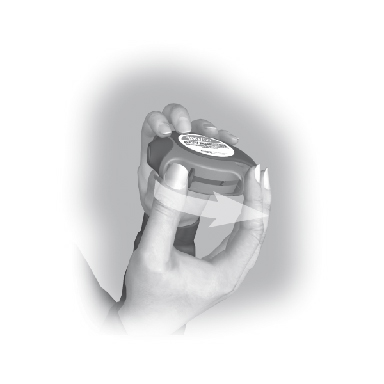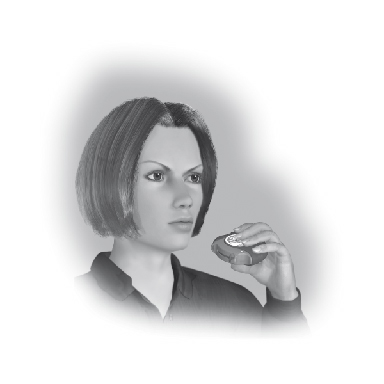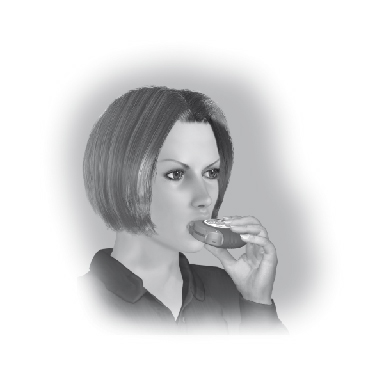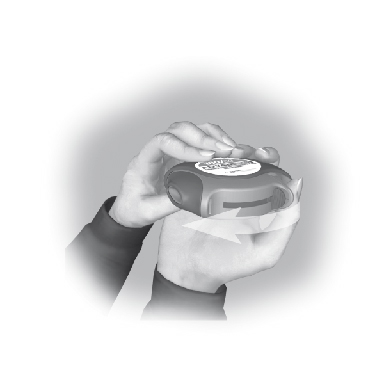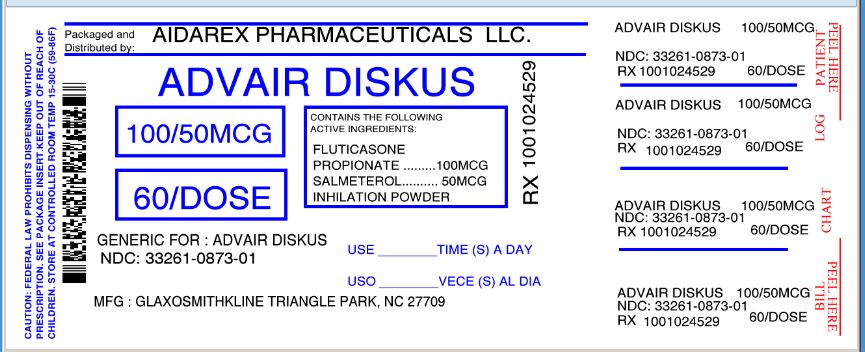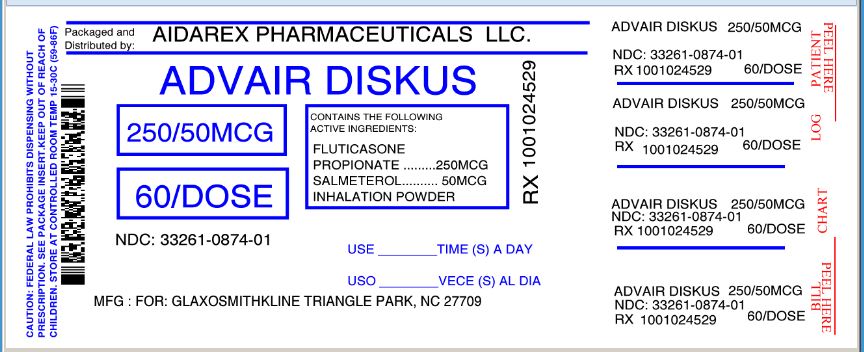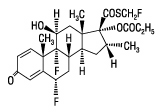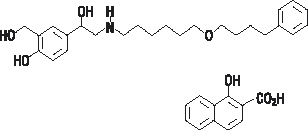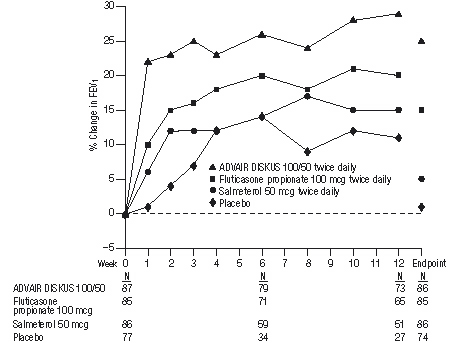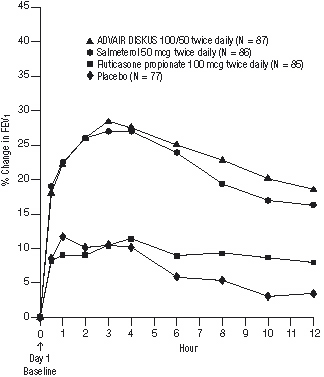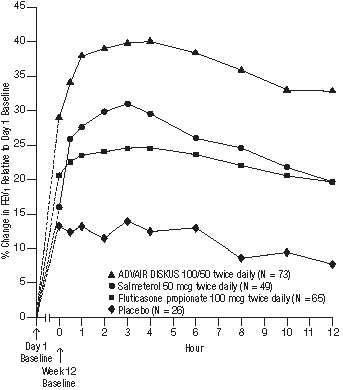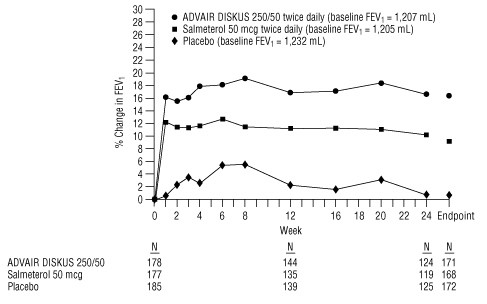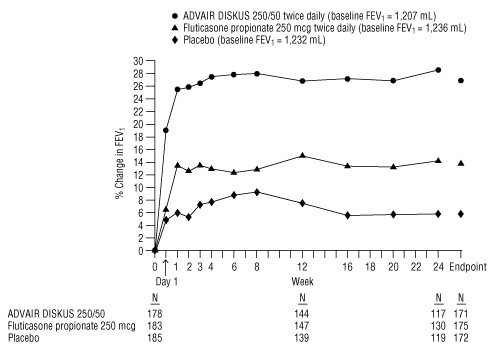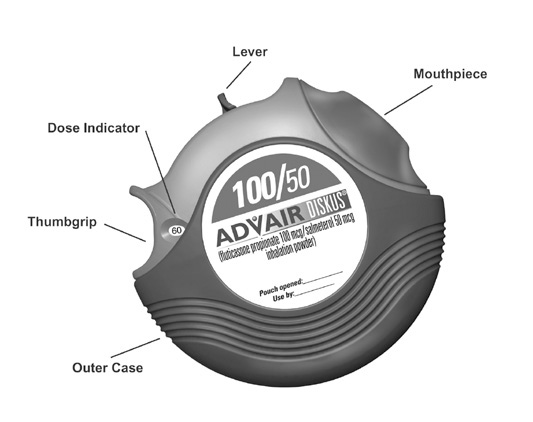 DRUG LABEL: ADVAIR
NDC: 33261-873 | Form: POWDER
Manufacturer: Aidarex Pharmaceuticals LLC
Category: prescription | Type: HUMAN PRESCRIPTION DRUG LABEL
Date: 20120910

ACTIVE INGREDIENTS: SALMETEROL XINAFOATE 50 ug/1 1; FLUTICASONE PROPIONATE 100 ug/1 1
INACTIVE INGREDIENTS: LACTOSE

HIGHLIGHTS OF PRESCRIBING INFORMATION

These highlights do not include all the information needed to use ADVAIR DISKUS safely and effectively. See full prescribing information for ADVAIR DISKUS.
ADVAIR DISKUS 100/50
(fluticasone propionate 100 mcg and salmeterol 50 mcg inhalation powder)
ADVAIR DISKUS 250/50
(fluticasone propionate 250 mcg and salmeterol 50 mcg inhalation powder)
ADVAIR DISKUS 500/50
(fluticasone propionate 500 mcg and salmeterol 50 mcg inhalation powder)
FOR ORAL INHALATION
Initial U.S. Approval: 2000

WARNING: ASTHMA-RELATED DEATH

See full prescribing information for complete boxed warning

- Long-acting beta2-adrenergic agonists (LABAs), such as salmeterol, one of the active ingredients in ADVAIR DISKUS, increase the risk of asthma-related death. A US study showed an increase in asthma-related deaths in patients receiving salmeterol (13 deaths out of 13,176 patients treated for 28 weeks on salmeterol versus 3 out of 13,179 patients on placebo). Currently available data are inadequate to determine whether concurrent use of inhaled corticosteroids or other long-term asthma control drugs mitigates the increased risk of asthma-related death from LABAs. Available data from controlled clinical trials suggest that LABAs increase the risk of asthma-related hospitalization in pediatric and adolescent patients. (5.1)
- When treating patients with asthma, only prescribe ADVAIR DISKUS for patients not adequately controlled on a long-term asthma control medication, such as an inhaled corticosteroid, or whose disease severity clearly warrants initiation of treatment with both an inhaled corticosteroid and a LABA. Once asthma control is achieved and maintained, assess the patient at regular intervals and step down therapy (e.g., discontinue ADVAIR DISKUS) if possible without loss of asthma control and maintain the patient on a long-term asthma control medication, such as an inhaled corticosteroid. Do not use ADVAIR DISKUS for patients whose asthma is adequately controlled on low- or medium-dose inhaled corticosteroids. (1.1, 5.1)

1 INDICATIONS AND USAGE

ADVAIR DISKUS is a combination product containing a corticosteroid and a LABA indicated for:

- Treatment of asthma in patients aged 4 years and older. (1.1)
- Maintenance treatment of airflow obstruction and reducing exacerbations in patients with chronic obstructive pulmonary disease (COPD). (1.2)

Important limitation:

- Not indicated for the relief of acute bronchospasm. (1.1, 1.2)

2 DOSAGE AND ADMINISTRATION

For oral inhalation only.

- Treatment of asthma in patients ≥12 years: 1 inhalation of ADVAIR DISKUS 100/50, 250/50, or 500/50 twice daily. Starting dosage is based on asthma severity. (2.1)
- Treatment of asthma in patients aged 4 to 11 years: 1 inhalation of ADVAIR DISKUS 100/50 twice daily. (2.1)
- Maintenance treatment of COPD: 1 inhalation of ADVAIR DISKUS 250/50 twice daily. (2.2)

3 DOSAGE FORMS AND STRENGTHS

DISKUS device containing a combination of fluticasone propionate (100, 250, or 500 mcg) and salmeterol (50 mcg) as an oral inhalation powder. (3)

4 CONTRAINDICATIONS

- Primary treatment of status asthmaticus or acute episodes of asthma or COPD requiring intensive measures. (4)
- Severe hypersensitivity to milk proteins. (4)

5 WARNINGS AND PRECAUTIONS

- Asthma-related death: LABAs increase the risk. Prescribe only for recommended patient populations. (5.1)
- Deterioration of disease and acute episodes: Do not initiate in acutely deteriorating asthma or to treat acute symptoms. (5.2)
- Use with additional LABA: Do not use in combination because of risk of overdose. (5.3)
- Localized infections: Candida albicans infection of the mouth and throat may occur. Monitor patients periodically for signs of adverse effects on the oral cavity. Advise patients to rinse the mouth following inhalation. (5.4)
- Pneumonia: Increased risk in patients with COPD. Monitor patients for signs and symptoms of pneumonia. (5.5)
- Immunosuppression: Potential worsening of infections (e.g., existing tuberculosis, fungal, bacterial, viral, or parasitic infection; ocular herpes simplex). Use with caution in patients with these infections. More serious or even fatal course of chickenpox or measles can occur in susceptible patients. (5.6)
- Transferring patients from systemic corticosteroids: Risk of impaired adrenal function when transferring from oral steroids. Taper patients slowly from systemic corticosteroids if transferring to ADVAIR DISKUS. (5.7)
- Hypercorticism and adrenal suppression: May occur with very high dosages or at the regular dosage in susceptible individuals. If such changes occur, discontinue ADVAIR DISKUS slowly. (5.8)
- Strong cytochrome P450 3A4 inhibitors (e.g., ritonavir): Risk of increased systemic corticosteroid and cardiovascular effects. Use not recommended with ADVAIR DISKUS. (5.9)
- Paradoxical bronchospasm: Discontinue ADVAIR DISKUS and institute alternative therapy if paradoxical bronchospasm occurs. (5.10)
- Patients with cardiovascular or central nervous system disorders: Use with caution because of beta-adrenergic stimulation. (5.12)
- Decreases in bone mineral density: Assess bone mineral density initially and periodically thereafter. (5.13)
- Effects on growth: Monitor growth of pediatric patients. (5.14)
- Glaucoma and cataracts: Close monitoring is warranted. (5.15)
- Metabolic effects: Be alert to eosinophilic conditions, hypokalemia, and hyperglycemia. (5.16, 5.18)
- Coexisting conditions: Use with caution in patients with convulsive disorders, thyrotoxicosis, diabetes mellitus, and ketoacidosis. (5.17)

6 ADVERSE REACTIONS

Most common adverse reactions (incidence ≥3%) are:

- Asthma: upper respiratory tract infection or inflammation, pharyngitis, dysphonia, oral candidiasis, bronchitis, cough, headaches, nausea and vomiting. (6.1)
- COPD: pneumonia, oral candidiasis, throat irritation, dysphonia, viral respiratory infections, headaches, musculoskeletal pain. (6.2)

To report SUSPECTED ADVERSE REACTIONS, contact GlaxoSmithKline at 1-888-825-5249 or FDA at 1-800-FDA-1088 or www.fda.gov/medwatch.

7 DRUG INTERACTIONS

- Strong cytochrome P450 3A4 inhibitors (e.g., ritonavir): Use not recommended. May cause systemic corticosteroid and cardiovascular effects. (7.1)
- Monoamine oxidase inhibitors and tricyclic antidepressants: Use with extreme caution. May potentiate effect of salmeterol on vascular system. (7.2)
- Beta-blockers: Use with caution. May block bronchodilatory effects of beta-agonists and produce severe bronchospasm. (7.3)
- Diuretics: Use with caution. Electrocardiographic changes and/or hypokalemia associated with nonpotassium-sparing diuretics may worsen with concomitant beta-agonists. (7.4)

8 USE IN SPECIFIC POPULATIONS

Hepatic impairment: Monitor patients for signs of increased drug exposure. (8.6)

FULL PRESCRIBING INFORMATION

WARNING: ASTHMA-RELATED DEATH

Long-acting beta2-adrenergic agonists (LABAs), such as salmeterol, one of the active ingredients in ADVAIR DISKUS®, increase the risk of asthma-related death. Data from a large placebo-controlled US study that compared the safety of salmeterol (SEREVENT®showed an increase in asthma-related deaths in patients receiving salmeterol (13 deaths out of 13,176 patients treated for 28 weeks on salmeterol versus 3 o Inhalation Aerosol) or placebo added to usual asthma therapy ut of 13,179 patients on placebo). Currently available data are inadequate to determine whether concurrent use of inhaled corticosteroids or other long-term asthma control drugs mitigates the increased risk of asthma-related death from LABAs. Available data from controlled clinical trials suggest that LABAs increase the risk of asthma-related hospitalization in pediatric and adolescent patients.

Therefore, when treating patients with asthma, physicians should only prescribe ADVAIR DISKUS for patients not adequately controlled on a long-term asthma control medication, such as an inhaled corticosteroid, or whose disease severity clearly warrants initiation of treatment with both an inhaled corticosteroid and a LABA. Once asthma control is achieved and maintained, assess the patient at regular intervals and step down therapy (e.g., discontinue ADVAIR DISKUS) if possible without loss of asthma control and maintain the patient on a long-term asthma control medication, such as an inhaled corticosteroid. Do not use ADVAIR DISKUS for patients whose asthma is adequately controlled on low- or medium-dose inhaled corticosteroids [see Warnings and Precautions (5.1)].

1 INDICATIONS AND USAGE

1.1 Treatment of Asthma

ADVAIR DISKUS is indicated for the treatment of asthma in patients aged 4 years and older.

Long-acting beta2-adrenergic agonists (LABAs), such as salmeterol, one of the active ingredients in ADVAIR DISKUS, increase the risk of asthma-related death. Available data from controlled clinical trials suggest that LABAs increase the risk of asthma-related hospitalization in pediatric and adolescent patients [see Warnings and Precautions (5.1)]. Therefore, when treating patients with asthma, physicians should only prescribe ADVAIR DISKUS for patients not adequately controlled on a long-term asthma control medication, such as an inhaled corticosteroid, or whose disease severity clearly warrants initiation of treatment with both an inhaled corticosteroid and a LABA. Once asthma control is achieved and maintained, assess the patient at regular intervals and step down therapy (e.g., discontinue ADVAIR DISKUS) if possible without loss of asthma control and maintain the patient on a long-term asthma control medication, such as an inhaled corticosteroid. Do not use ADVAIR DISKUS for patients whose asthma is adequately controlled on low- or medium-dose inhaled corticosteroids.

Important Limitation of Use: ADVAIR DISKUS is NOT indicated for the relief of acute bronchospasm.

1.2 Maintenance Treatment of Chronic Obstructive Pulmonary Disease

ADVAIR DISKUS 250/50 is indicated for the twice-daily maintenance treatment of airflow obstruction in patients with chronic obstructive pulmonary disease (COPD), including chronic bronchitis and/or emphysema. ADVAIR DISKUS 250/50 is also indicated to reduce exacerbations of COPD in patients with a history of exacerbations. ADVAIR DISKUS 250/50 twice daily is the only approved dosage for the treatment of COPD because an efficacy advantage of the higher strength ADVAIR DISKUS 500/50 over ADVAIR DISKUS 250/50 has not been demonstrated.

Important Limitation of Use: ADVAIR DISKUS is NOT indicated for the relief of acute bronchospasm.

2 DOSAGE AND ADMINISTRATION

ADVAIR DISKUS should be administered twice daily every day by the orally inhaled route only. After inhalation, the patient should rinse the mouth with water without swallowing [see Patient Counseling Information (17.4)].

More frequent administration or a higher number of inhalations (more than 1 inhalation twice daily) of the prescribed strength of ADVAIR DISKUS is not recommended as some patients are more likely to experience adverse effects with higher doses of salmeterol. Patients using ADVAIR DISKUS should not use additional LABAs for any reason. [See Warnings and Precautions (5.3, 5.12).]

2.1 Asthma

If asthma symptoms arise in the period between doses, an inhaled, short-acting beta2-agonist should be taken for immediate relief.

Adult and Adolescent Patients Aged 12 Years and Older: For patients aged 12 years and older, the dosage is 1 inhalation twice daily (morning and evening, approximately 12 hours apart).

The recommended starting dosages for ADVAIR DISKUS for patients aged 12 years and older are based upon patients’ asthma severity.

The maximum recommended dosage is ADVAIR DISKUS 500/50 twice daily.

Improvement in asthma control following inhaled administration of ADVAIR DISKUS can occur within 30 minutes of beginning treatment, although maximum benefit may not be achieved for 1 week or longer after starting treatment. Individual patients will experience a variable time to onset and degree of symptom relief.

For patients who do not respond adequately to the starting dosage after 2 weeks of therapy, replacing the current strength of ADVAIR DISKUS with a higher strength may provide additional improvement in asthma control.

If a previously effective dosage regimen of ADVAIR DISKUS fails to provide adequate improvement in asthma control, the therapeutic regimen should be reevaluated and additional therapeutic options (e.g., replacing the current strength of ADVAIR DISKUS with a higher strength, adding additional inhaled corticosteroid, initiating oral corticosteroids) should be considered.

Pediatric Patients Aged 4 to 11 Years: For patients with asthma aged 4 to 11 years who are not controlled on an inhaled corticosteroid, the dosage is 1 inhalation of ADVAIR DISKUS 100/50 twice daily (morning and evening, approximately 12 hours apart).

2.2 Chronic Obstructive Pulmonary Disease

The recommended dosage for patients with COPD is 1 inhalation of ADVAIR DISKUS 250/50 twice daily (morning and evening, approximately 12 hours apart).

If shortness of breath occurs in the period between doses, an inhaled, short-acting beta2-agonist should be taken for immediate relief.

3 DOSAGE FORMS AND STRENGTHS

Disposable purple device with 60 blisters containing a combination of fluticasone propionate (100, 250, or 500 mcg) and salmeterol (50 mcg) as an oral inhalation powder formulation. An institutional pack containing 14 blisters is also available.

4 CONTRAINDICATIONS

The use of ADVAIR DISKUS is contraindicated in the following conditions:

- Primary treatment of status asthmaticus or other acute episodes of asthma or COPD where intensive measures are required
- Severe hypersensitivity to milk proteins [see Warnings and Precautions (5.11), Description (11)]

5 WARNINGS AND PRECAUTIONS

5.1 Asthma-Related Death

LABAs, such as salmeterol, one of the active ingredients in ADVAIR DISKUS, increase the risk of asthma-related death. Currently available data are inadequate to determine whether concurrent use of inhaled corticosteroids or other long-term asthma control drugs mitigates the increased risk of asthma-related death from LABAs. Available data from controlled clinical trials suggest that LABAs increase the risk of asthma-related hospitalization in pediatric and adolescent patients. Therefore, when treating patients with asthma, physicians should only prescribe ADVAIR DISKUS for patients not adequately controlled on a long-term asthma control medication, such as an inhaled corticosteroid, or whose disease severity clearly warrants initiation of treatment with both an inhaled corticosteroid and a LABA. Once asthma control is achieved and maintained, assess the patient at regular intervals and step down therapy (e.g., discontinue ADVAIR DISKUS) if possible without loss of asthma control and maintain the patient on a long-term asthma control medication, such as an inhaled corticosteroid. Do not use ADVAIR DISKUS for patients whose asthma is adequately controlled on low- or medium-dose inhaled corticosteroids.

A large placebo-controlled US study that compared the safety of salmeterol with placebo, each added to usual asthma therapy, showed an increase in asthma-related deaths in patients receiving salmeterol. The Salmeterol Multi-center Asthma Research Trial (SMART) was a randomized double-blind study that enrolled LABA-naive patients with asthma to assess the safety of salmeterol (SEREVENT® Inhalation Aerosol) 42 mcg twice daily over 28 weeks compared with placebo when added to usual asthma therapy. A planned interim analysis was conducted when approximately half of the intended number of patients had been enrolled (N = 26,355), which led to premature termination of the study. The results of the interim analysis showed that patients receiving salmeterol were at increased risk for fatal asthma events (see Table 1 and Figure 1). In the total population, a higher rate of asthma-related death occurred in patients treated with salmeterol than those treated with placebo (0.10% versus 0.02%, relative risk: 4.37 [95% CI: 1.25, 15.34]).

Post-hoc subpopulation analyses were performed. In Caucasians, asthma-related death occurred at a higher rate in patients treated with salmeterol than in patients treated with placebo (0.07% versus 0.01%, relative risk: 5.82 [95% CI: 0.70, 48.37]). In African Americans also, asthma-related death occurred at a higher rate in patients treated with salmeterol than those treated with placebo (0.31% versus 0.04%, relative risk: 7.26 [95% CI: 0.89, 58.94]). Although the relative risks of asthma-related death were similar in Caucasians and African Americans, the estimate of excess deaths in patients treated with salmeterol was greater in African Americans because there was a higher overall rate of asthma-related death in African American patients (see Table 1). Given the similar basic mechanisms of action of beta2-agonists, the findings seen in the SMART study are considered a class effect.

Post-hoc analyses in pediatric patients aged 12 to 18 years were also performed. Pediatric patients accounted for approximately 12% of patients in each treatment arm. Respiratory-related death or life-threatening experience occurred at a similar rate in the salmeterol group (0.12% [2/1,653]) and the placebo group (0.12% [2/1,622]; relative risk: 1.0 [95% CI: 0.1, 7.2]). All-cause hospitalization, however, was increased in the salmeterol group (2% [35/1,653]) versus the placebo group (<1% [16/1,622]; relative risk: 2.1 [95% CI: 1.1, 3.7]).

The data from the SMART study are not adequate to determine whether concurrent use of inhaled corticosteroids, such as fluticasone propionate, the other active ingredient in ADVAIR DISKUS, or other long-term asthma control therapy mitigates the risk of asthma-related death.

Table 1. Asthma-Related Deaths in the 28-Week Salmeterol Multi-center Asthma Research Trial (SMART)
 | Salmeterol; n (%a) | Placebo; n (%a) | Relative Riskb; (95% Confidence; Interval) | Excess Deaths; Expressed per; 10,000 Patientsc; (95% Confidence; Interval)
Total Populationd
Salmeterol: N = 13,176 | 13 (0.10%) |  | 4.37 (1.25, 15.34) | 8 (3, 13)
Placebo: N = 13,179 |  | 3 (0.02%)
Caucasian
Salmeterol: N = 9,281 | 6 (0.07%) |  | 5.82 (0.70, 48.37) | 6 (1, 10)
Placebo: N = 9,361 |  | 1 (0.01%)
African American
Salmeterol: N = 2,366 | 7 (0.31%) |  | 7.26 (0.89, 58.94) | 27 (8, 46)
Placebo: N = 2,319 |  | 1 (0.04%)
aLife-table 28-week estimate, adjusted according to the patients’ actual lengths of exposure to study treatment to account for early withdrawal of patients from the study.
bRelative risk is the ratio of the rate of asthma-related death in the salmeterol group and the rate in the placebo group. The relative risk indicates how many more times likely an asthma-related death occurred in the salmeterol group than in the placebo group in a 28-week treatment period.
cEstimate of the number of additional asthma-related deaths in patients treated with salmeterol in SMART, assuming 10,000 patients received salmeterol for a 28-week treatment period. Estimate calculated as the difference between the salmeterol and placebo groups in the rates of asthma-related death multiplied by 10,000.
dThe Total Population includes the following ethnic origins listed on the case report form: Caucasian, African American, Hispanic, Asian, and “Other.” In addition, the Total Population includes those patients whose ethnic origin was not reported. The results for Caucasian and African American subpopulations are shown above. No asthma-related deaths occurred in the Hispanic (salmeterol n = 996, placebo n = 999), Asian (salmeterol n = 173, placebo n = 149), or “Other” (salmeterol n = 230, placebo n = 224) subpopulations. One asthma-related death occurred in the placebo group in the subpopulation whose ethnic origin was not reported (salmeterol n = 130, placebo n = 127).

Figure 1. Cumulative Incidence of Asthma-Related Deaths in the 28-Week Salmeterol Multi-center Asthma Research Trial (SMART), by Duration of Treatment

A 16-week clinical study performed in the United Kingdom, the Salmeterol Nationwide Surveillance (SNS) study, showed results similar to the SMART study. In the SNS study, the rate of asthma-related death was numerically, though not statistically significantly, greater in patients with asthma treated with salmeterol (42 mcg twice daily) than those treated with albuterol (180 mcg 4 times daily) added to usual asthma therapy.

The SNS and SMART studies enrolled patients with asthma. No studies have been conducted that were primarily designed to determine whether the rate of death in patients with COPD is increased by LABAs.

5.2 Deterioration of Disease and Acute Episodes

ADVAIR DISKUS should not be initiated in patients during rapidly deteriorating or potentially life-threatening episodes of asthma or COPD. ADVAIR DISKUS has not been studied in patients with acutely deteriorating asthma or COPD. The initiation of ADVAIR DISKUS in this setting is not appropriate.

Serious acute respiratory events, including fatalities, have been reported when salmeterol, a component of ADVAIR DISKUS, has been initiated in patients with significantly worsening or acutely deteriorating asthma. In most cases, these have occurred in patients with severe asthma (e.g., patients with a history of corticosteroid dependence, low pulmonary function, intubation, mechanical ventilation, frequent hospitalizations, previous life-threatening acute asthma exacerbations) and in some patients with acutely deteriorating asthma (e.g., patients with significantly increasing symptoms; increasing need for inhaled, short-acting beta2-agonists; decreasing response to usual medications; increasing need for systemic corticosteroids; recent emergency room visits; deteriorating lung function). However, these events have occurred in a few patients with less severe asthma as well. It was not possible from these reports to determine whether salmeterol contributed to these events.

Increasing use of inhaled, short-acting beta2-agonists is a marker of deteriorating asthma. In this situation, the patient requires immediate reevaluation with reassessment of the treatment regimen, giving special consideration to the possible need for replacing the current strength of ADVAIR DISKUS with a higher strength, adding additional inhaled corticosteroid, or initiating systemic corticosteroids. Patients should not use more than 1 inhalation twice daily (morning and evening) of ADVAIR DISKUS.

ADVAIR DISKUS should not be used for the relief of acute symptoms, i.e., as rescue therapy for the treatment of acute episodes of bronchospasm. An inhaled, short-acting beta2-agonist, not ADVAIR DISKUS, should be used to relieve acute symptoms such as shortness of breath. When prescribing ADVAIR DISKUS, the physician must also provide the patient with an inhaled, short-acting beta2-agonist (e.g., albuterol) for treatment of acute symptoms, despite regular twice-daily (morning and evening) use of ADVAIR DISKUS.

When beginning treatment with ADVAIR DISKUS, patients who have been taking oral or inhaled, short-acting beta2-agonists on a regular basis (e.g., 4 times a day) should be instructed to discontinue the regular use of these drugs.

5.3 Excessive Use of ADVAIR DISKUS and Use With Other Long-Acting Beta2-Agonists

As with other inhaled drugs containing beta2-adrenergic agents, ADVAIR DISKUS should not be used more often than recommended, at higher doses than recommended, or in conjunction with other medications containing LABAs, as an overdose may result. Clinically significant cardiovascular effects and fatalities have been reported in association with excessive use of inhaled sympathomimetic drugs. Patients using ADVAIR DISKUS should not use an additional LABA (e.g., salmeterol, formoterol fumarate, arformoterol tartrate) for any reason, including prevention of exercise-induced bronchospasm (EIB) or the treatment of asthma or COPD.

5.4 Local Effects

In clinical studies, the development of localized infections of the mouth and pharynx with Candida albicans has occurred in patients treated with ADVAIR DISKUS. When such an infection develops, it should be treated with appropriate local or systemic (i.e., oral antifungal) therapy while treatment with ADVAIR DISKUS continues, but at times therapy with ADVAIR DISKUS may need to be interrupted. Patients should rinse the mouth after inhalation of ADVAIR DISKUS.

5.5 Pneumonia

Physicians should remain vigilant for the possible development of pneumonia in patients with COPD as the clinical features of pneumonia and exacerbations frequently overlap.

Lower respiratory tract infections, including pneumonia, have been reported in patients with COPD following the inhaled administration of corticosteroids, including fluticasone propionate and ADVAIR DISKUS. In 2 replicate 12-month studies of 1,579 patients with COPD, there was a higher incidence of pneumonia reported in patients receiving ADVAIR DISKUS 250/50 (7%) than in those receiving salmeterol 50 mcg (3%). The incidence of pneumonia in the patients treated with ADVAIR DISKUS was higher in patients over 65 years of age (9%) compared with the incidence in patients less than 65 years of age (4%). [See Adverse Reactions (6.2), Use in Specific Populations (8.5).]

In a 3-year study of 6,184 patients with COPD, there was a higher incidence of pneumonia reported in patients receiving ADVAIR DISKUS 500/50 compared with placebo (16% with ADVAIR DISKUS 500/50, 14% with fluticasone propionate 500 mcg, 11% with salmeterol 50 mcg, and 9% with placebo). Similar to what was seen in the 1-year studies with ADVAIR DISKUS 250/50, the incidence of pneumonia was higher in patients over 65 years of age (18% with ADVAIR DISKUS 500/50 versus 10% with placebo) compared with patients less than 65 years of age (14% with ADVAIR DISKUS 500/50 versus 8% with placebo). [See Adverse Reactions (6.2), Use in Specific Populations (8.5).]

5.6 Immunosuppression

Persons who are using drugs that suppress the immune system are more susceptible to infections than healthy individuals. Chickenpox and measles, for example, can have a more serious or even fatal course in susceptible children or adults using corticosteroids. In such children or adults who have not had these diseases or been properly immunized, particular care should be taken to avoid exposure. How the dose, route, and duration of corticosteroid administration affect the risk of developing a disseminated infection is not known. The contribution of the underlying disease and/or prior corticosteroid treatment to the risk is also not known. If a patient is exposed to chickenpox, prophylaxis with varicella zoster immune globulin (VZIG) may be indicated. If a patient is exposed to measles, prophylaxis with pooled intramuscular immunoglobulin (IG) may be indicated. (See the respective package inserts for complete VZIG and IG prescribing information.) If chickenpox develops, treatment with antiviral agents may be considered.

Inhaled corticosteroids should be used with caution, if at all, in patients with active or quiescent tuberculosis infections of the respiratory tract; untreated systemic fungal, bacterial, viral, or parasitic infections; or ocular herpes simplex.

5.7 Transferring Patients From Systemic Corticosteroid Therapy

Particular care is needed for patients who have been transferred from systemically active corticosteroids to inhaled corticosteroids because deaths due to adrenal insufficiency have occurred in patients with asthma during and after transfer from systemic corticosteroids to less systemically available inhaled corticosteroids. After withdrawal from systemic corticosteroids, a number of months are required for recovery of hypothalamic-pituitary-adrenal (HPA) function.

Patients who have been previously maintained on 20 mg or more per day of prednisone (or its equivalent) may be most susceptible, particularly when their systemic corticosteroids have been almost completely withdrawn. During this period of HPA suppression, patients may exhibit signs and symptoms of adrenal insufficiency when exposed to trauma, surgery, or infection (particularly gastroenteritis) or other conditions associated with severe electrolyte loss. Although ADVAIR DISKUS may provide control of asthma symptoms during these episodes, in recommended doses it supplies less than normal physiological amounts of glucocorticoid systemically and does NOT provide the mineralocorticoid activity that is necessary for coping with these emergencies.

During periods of stress or a severe asthma attack, patients who have been withdrawn from systemic corticosteroids should be instructed to resume oral corticosteroids (in large doses) immediately and to contact their physicians for further instruction. These patients should also be instructed to carry a warning card indicating that they may need supplementary systemic corticosteroids during periods of stress or a severe asthma attack.

Patients requiring oral corticosteroids should be weaned slowly from systemic corticosteroid use after transferring to ADVAIR DISKUS. Prednisone reduction can be accomplished by reducing the daily prednisone dose by 2.5 mg on a weekly basis during therapy with ADVAIR DISKUS. Lung function (mean forced expiratory volume in 1 second [FEV1] or morning peak expiratory flow [PEF]), beta-agonist use, and asthma symptoms should be carefully monitored during withdrawal of oral corticosteroids. In addition to monitoring asthma signs and symptoms, patients should be observed for signs and symptoms of adrenal insufficiency, such as fatigue, lassitude, weakness, nausea and vomiting, and hypotension.

Transfer of patients from systemic corticosteroid therapy to inhaled corticosteroids or ADVAIR DISKUS may unmask conditions previously suppressed by the systemic corticosteroid therapy (e.g., rhinitis, conjunctivitis, eczema, arthritis, eosinophilic conditions). Some patients may experience symptoms of systemically active corticosteroid withdrawal (e.g., joint and/or muscular pain, lassitude, depression) despite maintenance or even improvement of respiratory function.

5.8 Hypercorticism and Adrenal Suppression

Fluticasone propionate, a component of ADVAIR DISKUS, will often help control asthma symptoms with less suppression of HPA function than therapeutically equivalent oral doses of prednisone. Since fluticasone propionate is absorbed into the circulation and can be systemically active at higher doses, the beneficial effects of ADVAIR DISKUS in minimizing HPA dysfunction may be expected only when recommended dosages are not exceeded and individual patients are titrated to the lowest effective dose. A relationship between plasma levels of fluticasone propionate and inhibitory effects on stimulated cortisol production has been shown after 4 weeks of treatment with fluticasone propionate inhalation aerosol. Since individual sensitivity to effects on cortisol production exists, physicians should consider this information when prescribing ADVAIR DISKUS.

Because of the possibility of systemic absorption of inhaled corticosteroids, patients treated with ADVAIR DISKUS should be observed carefully for any evidence of systemic corticosteroid effects. Particular care should be taken in observing patients postoperatively or during periods of stress for evidence of inadequate adrenal response.

It is possible that systemic corticosteroid effects such as hypercorticism and adrenal suppression (including adrenal crisis) may appear in a small number of patients, particularly when fluticasone propionate is administered at higher than recommended doses over prolonged periods of time. If such effects occur, the dosage of ADVAIR DISKUS should be reduced slowly, consistent with accepted procedures for reducing systemic corticosteroids and for management of asthma symptoms.

5.9 Drug Interactions With Strong Cytochrome P450 3A4 Inhibitors

The use of strong cytochrome P450 3A4 (CYP3A4) inhibitors (e.g., ritonavir, atazanavir, clarithromycin, indinavir, itraconazole, nefazodone, nelfinavir, saquinavir, ketoconazole, telithromycin) with ADVAIR DISKUS is not recommended because increased systemic corticosteroid and increased cardiovascular adverse effects may occur [see Drug interactions (7.1), Clinical Pharmacology (12.3)].

5.10 Paradoxical Bronchospasm and Upper Airway Symptoms

As with other inhaled medications, ADVAIR DISKUS can produce paradoxical bronchospasm, which may be life threatening. If paradoxical bronchospasm occurs following dosing with ADVAIR DISKUS, it should be treated immediately with an inhaled, short-acting bronchodilator; ADVAIR DISKUS should be discontinued immediately; and alternative therapy should be instituted. Upper airway symptoms of laryngeal spasm, irritation, or swelling, such as stridor and choking, have been reported in patients receiving fluticasone propionate and salmeterol.

5.11 Immediate Hypersensitivity Reactions

Immediate hypersensitivity reactions may occur after administration of ADVAIR DISKUS, as demonstrated by cases of urticaria, angioedema, rash, and bronchospasm. There have been reports of anaphylactic reactions in patients with severe milk protein allergy; therefore, patients with severe milk protein allergy should not take ADVAIR DISKUS [see Contraindications (4)].

5.12 Cardiovascular and Central Nervous System Effects

Excessive beta-adrenergic stimulation has been associated with seizures, angina, hypertension or hypotension, tachycardia with rates up to 200 beats/min, arrhythmias, nervousness, headache, tremor, palpitation, nausea, dizziness, fatigue, malaise, and insomnia [see Overdosage (10)]. Therefore, ADVAIR DISKUS, like all products containing sympathomimetic amines, should be used with caution in patients with cardiovascular disorders, especially coronary insufficiency, cardiac arrhythmias, and hypertension.

Salmeterol, a component of ADVAIR DISKUS, can produce a clinically significant cardiovascular effect in some patients as measured by pulse rate, blood pressure, and/or symptoms. Although such effects are uncommon after administration of salmeterol at recommended doses, if they occur, the drug may need to be discontinued. In addition, beta-agonists have been reported to produce electrocardiogram (ECG) changes, such as flattening of the T wave, prolongation of the QTc interval, and ST segment depression. The clinical significance of these findings is unknown. Large doses of inhaled or oral salmeterol (12 to 20 times the recommended dose) have been associated with clinically significant prolongation of the QTc interval, which has the potential for producing ventricular arrhythmias. Fatalities have been reported in association with excessive use of inhaled sympathomimetic drugs.

5.13 Reduction in Bone Mineral Density

Decreases in bone mineral density (BMD) have been observed with long-term administration of products containing inhaled corticosteroids. The clinical significance of small changes in BMD with regard to long-term consequences such as fracture is unknown. Patients with major risk factors for decreased bone mineral content, such as prolonged immobilization, family history of osteoporosis, post-menopausal status, tobacco use, advanced age, poor nutrition, or chronic use of drugs that can reduce bone mass (e.g., anticonvulsants, oral corticosteroids) should be monitored and treated with established standards of care. Since patients with COPD often have multiple risk factors for reduced BMD, assessment of BMD is recommended prior to initiating ADVAIR DISKUS and periodically thereafter. If significant reductions in BMD are seen and ADVAIR DISKUS is still considered medically important for that patient’s COPD therapy, use of medication to treat or prevent osteoporosis should be strongly considered.

2-Year Fluticasone Propionate Study: A 2-year study of 160 patients (females aged 18 to 40 years, males 18 to 50) with asthma receiving CFC-propelled fluticasone propionate inhalation aerosol 88 or 440 mcg twice daily demonstrated no statistically significant changes in BMD at any time point (24, 52, 76, and 104 weeks of double-blind treatment) as assessed by dual-energy x-ray absorptiometry at lumbar regions L1 through L4.

3-Year Bone Mineral Density Study: Effects of treatment with ADVAIR DISKUS 250/50 or salmeterol 50 mcg on BMD at the L1-L4 lumbar spine and total hip were evaluated in 186 patients with COPD (aged 43 to 87 years) in a 3-year double-blind study. Of those enrolled, 108 patients (72 males and 36 females) were followed for the entire 3 years. BMD evaluations were conducted at baseline and at 6-month intervals. Conclusions cannot be drawn from this study regarding BMD decline in patients treated with ADVAIR DISKUS versus salmeterol due to the inconsistency of treatment differences across gender and between lumbar spine and total hip.

In this study there were 7 non-traumatic fractures reported in 5 patients treated with ADVAIR DISKUS and 1 non-traumatic fracture in 1 patient treated with salmeterol. None of the non-traumatic fractures occurred in the vertebrae, hip, or long bones.

3-Year Survival Study: Effects of treatment with ADVAIR DISKUS 500/50, fluticasone propionate 500 mcg, salmeterol 50 mcg, or placebo on BMD was evaluated in a subset of 658 patients (females and males aged 40 to 80 years) with COPD in the 3-year survival study. BMD evaluations were conducted at baseline and at 48, 108, and 158 weeks. Conclusions cannot be drawn from this study because of the large number of drop outs (>50%) before the end of the follow-up and the maldistribution of covariates among the treatment groups that can affect BMD.

Fracture risk was estimated for the entire population of patients with COPD in the survival study (N = 6,184). The probability of a fracture over 3 years was 6.3% for ADVAIR DISKUS, 5.4% for fluticasone propionate, 5.1% for salmeterol, and 5.1% for placebo.

5.14 Effect on Growth

Orally inhaled corticosteroids may cause a reduction in growth velocity when administered to pediatric patients. Monitor the growth of pediatric patients receiving ADVAIR DISKUS routinely (e.g., via stadiometry). To minimize the systemic effects of orally inhaled corticosteroids, including ADVAIR DISKUS, titrate each patient’s dose to the lowest dosage that effectively controls his/her symptoms. [See Dosage and Administration (2.1), Use in Specific Populations (8.4).]

5.15 Glaucoma and Cataracts

Glaucoma, increased intraocular pressure, and cataracts have been reported in patients with asthma and COPD following the long-term administration of inhaled corticosteroids, including fluticasone propionate, a component of ADVAIR DISKUS. Therefore, close monitoring is warranted in patients with a change in vision or with a history of increased intraocular pressure, glaucoma, and/or cataracts.

Effects of treatment with ADVAIR DISKUS 500/50, fluticasone propionate 500 mcg, salmeterol 50 mcg, or placebo on development of cataracts or glaucoma was evaluated in a subset of 658 patients with COPD in the 3-year survival study. Ophthalmic examinations were conducted at baseline and at 48, 108, and 158 weeks. Conclusions about cataracts cannot be drawn from this study because the high incidence of cataracts at baseline (61% to 71%) resulted in an inadequate number of patients treated with ADVAIR DISKUS 500/50 who were eligible and available for evaluation of cataracts at the end of the study (n = 53). The incidence of newly diagnosed glaucoma was 2% with ADVAIR DISKUS 500/50, 5% with fluticasone propionate, 0% with salmeterol, and 2% with placebo.

5.16 Eosinophilic Conditions and Churg-Strauss Syndrome

In rare cases, patients on inhaled fluticasone propionate may present with systemic eosinophilic conditions. Some of these patients have clinical features of vasculitis consistent with Churg-Strauss syndrome, a condition that is often treated with systemic corticosteroid therapy. These events usually, but not always, have been associated with the reduction and/or withdrawal of oral corticosteroid therapy following the introduction of fluticasone propionate. Cases of serious eosinophilic conditions have also been reported with other inhaled corticosteroids in this clinical setting. Physicians should be alert to eosinophilia, vasculitic rash, worsening pulmonary symptoms, cardiac complications, and/or neuropathy presenting in their patients. A causal relationship between fluticasone propionate and these underlying conditions has not been established.

5.17 Coexisting Conditions

ADVAIR DISKUS, like all medications containing sympathomimetic amines, should be used with caution in patients with convulsive disorders or thyrotoxicosis and in those who are unusually responsive to sympathomimetic amines. Doses of the related beta2-adrenoceptor agonist albuterol, when administered intravenously, have been reported to aggravate preexisting diabetes mellitus and ketoacidosis.

5.18 Hypokalemia and Hyperglycemia

Beta-adrenergic agonist medications may produce significant hypokalemia in some patients, possibly through intracellular shunting, which has the potential to produce adverse cardiovascular effects [see Clinical Pharmacology (12.2)]. The decrease in serum potassium is usually transient, not requiring supplementation. Clinically significant changes in blood glucose and/or serum potassium were seen infrequently during clinical studies with ADVAIR DISKUS at recommended doses.

6 ADVERSE REACTIONS

LABAs, such as salmeterol, one of the active ingredients in ADVAIR DISKUS, increase the risk of asthma-related death. Data from a large placebo-controlled US study that compared the safety of salmeterol (SEREVENT Inhalation Aerosol) or placebo added to usual asthma therapy showed an increase in asthma-related deaths in patients receiving salmeterol [see Warnings and Precautions (5.1)]. Currently available data are inadequate to determine whether concurrent use of inhaled corticosteroids or other long-term asthma control drugs mitigates the increased risk of asthma-related death from LABA. Available data from controlled clinical trials suggest that LABA increase the risk of asthma-related hospitalization in pediatric and adolescent patients.

Systemic and local corticosteroid use may result in the following:

- Candida albicans infection [see Warnings and Precautions (5.4)]
- Pneumonia in patients with COPD [see Warnings and Precautions (5.5)]
- Immunosuppression [see Warnings and Precautions (5.6)]
- Hypercorticism and adrenal suppression [see Warnings and Precautions (5.8)]
- Growth effects [see Warnings and Precautions (5.14)]
- Glaucoma and cataracts [see Warnings and Precautions (5.15)]

Because clinical trials are conducted under widely varying conditions, adverse reaction rates observed in the clinical trials of a drug cannot be directly compared with rates in the clinical trials of another drug and may not reflect the rates observed in practice.

6.1 Clinical Trials Experience in Asthma

Adult and Adolescent Patients Aged 12 Years and Older: The incidence of adverse reactions associated with ADVAIR DISKUS in Table 2 is based upon 2 placebo-controlled, 12-week, US clinical studies (Studies 1 and 2). A total of 705 adult and adolescent patients (349 females and 356 males) previously treated with salmeterol or inhaled corticosteroids were treated twice daily with ADVAIR DISKUS (100/50- or 250/50-mcg doses), fluticasone propionate inhalation powder (100- or 250-mcg doses), salmeterol inhalation powder 50 mcg, or placebo. The average duration of exposure was 60 to 79 days in the active treatment groups compared with 42 days in the placebo group.

Table 2. Adverse Reactions With ≥3% Incidence With ADVAIR DISKUS in Adult and Adolescent Patients With Asthma
Adverse Event | ADVAIR; DISKUS; 100/50; (N = 92); % | ADVAIR; DISKUS; 250/50; (N = 84); % | Fluticasone; Propionate; 100 mcg; (N = 90); % | Fluticasone; Propionate; 250 mcg; (N = 84); % | Salmeterol; 50 mcg; (N = 180); % | Placebo; (N = 175); %
Ear, nose, & throat
Upper respiratory tract; infection | 27 | 21 | 29 | 25 | 19 | 14
Pharyngitis | 13 | 10 | 7 | 12 | 8 | 6
Upper respiratory; inflammation | 7 | 6 | 7 | 8 | 8 | 5
Sinusitis | 4 | 5 | 6 | 1 | 3 | 4
Hoarseness/dysphonia | 5 | 2 | 2 | 4 | <1 | <1
Oral candidiasis | 1 | 4 | 2 | 2 | 0 | 0
Lower respiratory
Viral respiratory infections | 4 | 4 | 4 | 10 | 6 | 3
Bronchitis | 2 | 8 | 1 | 2 | 2 | 2
Cough | 3 | 6 | 0 | 0 | 3 | 2
Neurology
Headaches | 12 | 13 | 14 | 8 | 10 | 7
Gastrointestinal
Nausea & vomiting | 4 | 6 | 3 | 4 | 1 | 1
Gastrointestinal discomfort; & pain | 4 | 1 | 0 | 2 | 1 | 1
Diarrhea | 4 | 2 | 2 | 2 | 1 | 1
Viral gastrointestinal; infections | 3 | 0 | 3 | 1 | 2 | 2
Non-site specific
Candidiasis unspecified site | 3 | 0 | 1 | 4 | 0 | 1
Musculoskeletal
Musculoskeletal pain | 4 | 2 | 1 | 5 | 3 | 3

The types of adverse reactions and events reported in Study 3, a 28-week, non-US clinical study of 503 patients previously treated with inhaled corticosteroids who were treated twice daily with ADVAIR DISKUS 500/50, fluticasone propionate inhalation powder 500 mcg and salmeterol inhalation powder 50 mcg used concurrently, or fluticasone propionate inhalation powder 500 mcg, were similar to those reported in Table 2.

Additional Adverse Reactions: Other adverse reactions not previously listed, whether considered drug-related or not by the investigators, that were reported more frequently by patients with asthma treated with ADVAIR DISKUS compared with patients treated with placebo include the following: lymphatic signs and symptoms; muscle injuries; fractures; wounds and lacerations; contusions and hematomas; ear signs and symptoms; nasal signs and symptoms; nasal sinus disorders; keratitis and conjunctivitis; dental discomfort and pain; gastrointestinal signs and symptoms; oral ulcerations; oral discomfort and pain; lower respiratory signs and symptoms; pneumonia; muscle stiffness, tightness, and rigidity; bone and cartilage disorders; sleep disorders; compressed nerve syndromes; viral infections; pain; chest symptoms; fluid retention; bacterial infections; unusual taste; viral skin infections; skin flakiness and acquired ichthyosis; disorders of sweat and sebum.

Pediatric Patients Aged 4 to 11 Years: The safety data for pediatric patients aged 4 to 11 years is based upon 1 US trial of 12 weeks’ treatment duration. A total of 203 patients (74 females and 129 males) who were receiving inhaled corticosteroids at study entry were randomized to either ADVAIR DISKUS 100/50 or fluticasone propionate inhalation powder 100 mcg twice daily. Common adverse reactions (≥3% and greater than placebo) seen in the pediatric patients but not reported in the adult and adolescent clinical trials include: throat irritation and ear, nose, and throat infections.

Laboratory Test Abnormalities: Elevation of hepatic enzymes was reported in ≥1% of patients in clinical trials. The elevations were transient and did not lead to discontinuation from the studies. In addition, there were no clinically relevant changes noted in glucose or potassium.

6.2 Clinical Trials Experience in Chronic Obstructive Pulmonary Disease

Short-Term (6 Months to 1 Year) Trials: The short-term safety data are based on exposure to ADVAIR DISKUS 250/50 twice daily in one 6-month and two 1-year clinical trials. In the 6-month trial, a total of 723 adult patients (266 females and 457 males) were treated twice daily with ADVAIR DISKUS 250/50, fluticasone propionate inhalation powder 250 mcg, salmeterol inhalation powder, or placebo. The mean age of the patients was 64, and the majority (93%) was Caucasian. In this trial, 70% of the patients treated with ADVAIR DISKUS reported an adverse reaction compared with 64% on placebo. The average duration of exposure to ADVAIR DISKUS 250/50 was 141.3 days compared with 131.6 days for placebo. The incidence of adverse reactions in the 6-month study is shown in Table 3.

Table 3. Overall Adverse Reactions With ≥3% Incidence With ADVAIR DISKUS 250/50 in Patients With Chronic Obstructive Pulmonary Disease Associated With Chronic Bronchitis
Adverse Event | ADVAIR; DISKUS; 250/50; (N = 178); % | Fluticasone; Propionate; 250 mcg; (N = 183); % | Salmeterol; 50 mcg; (N = 177); % | Placebo; (N = 185); %
Ear, nose, & throat
Candidiasis mouth/throat | 10 | 6 | 3 | 1
Throat irritation | 8 | 5 | 4 | 7
Hoarseness/dysphonia | 5 | 3 | <1 | 0
Sinusitis | 3 | 8 | 5 | 3
Lower respiratory
Viral respiratory infections | 6 | 4 | 3 | 3
Neurology
Headaches | 16 | 11 | 10 | 12
Dizziness | 4 | <1 | 3 | 2
Non-site specific
Fever | 4 | 3 | 0 | 3
Malaise & fatigue | 3 | 2 | 2 | 3
Musculoskeletal
Musculoskeletal pain | 9 | 8 | 12 | 9
Muscle cramps & spasms | 3 | 3 | 1 | 1

In the two 1-year studies, ADVAIR DISKUS 250/50 was compared with salmeterol in 1,579 patients (863 males and 716 females). The mean age of the patients was 65, and the majority (94%) was Caucasian. To be enrolled, all of the patients had to have had a COPD exacerbation in the previous 12 months. In this trial, 88% of the patients treated with ADVAIR DISKUS and 86% of the patients treated with salmeterol reported an adverse event. The most common events that occurred with a frequency of >5% and more frequently in the patients treated with ADVAIR DISKUS were nasopharyngitis, upper respiratory tract infection, nasal congestion, back pain, sinusitis, dizziness, nausea, pneumonia, candidiasis, and dysphonia. Overall, 55 (7%) of the patients treated with ADVAIR DISKUS and 25 (3%) of the patients treated with salmeterol developed pneumonia.

The incidence of pneumonia was higher in patients over 65 years of age, 9% in the patients treated with ADVAIR DISKUS compared with 4% in the patients treated with ADVAIR DISKUS less than 65 years of age. In the patients treated with salmeterol, the incidence of pneumonia was the same (3%) in both age-groups. [See Warnings and Precautions (5.5), Use in Specific Populations (8.5).]

Long-Term (3-Year) Trial: The safety of ADVAIR DISKUS 500/50 was evaluated in a randomized, double-blind, placebo-controlled, multicenter, international, 3-year study in 6,184 adult patients with COPD (4,684 males and 1,500 females). The mean age of the patients was 65, and the majority (82%) was Caucasian. The distribution of adverse events was similar to that seen in the 1-year trials with ADVAIR DISKUS 250/50. In addition, pneumonia was reported in a significantly increased number of patients treated with ADVAIR DISKUS 500/50 and fluticasone propionate 500 mcg (16% and 14%, respectively) compared with patients treated with salmeterol 50 mcg or placebo (11% and 9%, respectively). When adjusted for time on treatment, the rates of pneumonia were 84 and 88 events per 1,000 treatment-years in the groups treated with fluticasone propionate 500 mcg and with ADVAIR DISKUS 500/50, respectively, compared with 52 events per 1,000 treatment-years in the salmeterol and placebo groups. Similar to what was seen in the 1-year studies with ADVAIR DISKUS 250/50, the incidence of pneumonia was higher in patients over 65 years of age (18% with ADVAIR DISKUS 500/50 versus 10% with placebo) compared with patients less than 65 years of age (14% with ADVAIR DISKUS 500/50 versus 8% with placebo). [See Warnings and Precautions (5.5), Use in Specific Populations (8.5).]

Additional Adverse Reactions: Other adverse reactions not previously listed, whether considered drug-related or not by the investigators, that were reported more frequently by patients with COPD treated with ADVAIR DISKUS compared with patients treated with placebo include the following: syncope; ear, nose, and throat infections; ear signs and symptoms; laryngitis; nasal congestion/blockage; nasal sinus disorders; pharyngitis/throat infection; hypothyroidism; dry eyes; eye infections; gastrointestinal signs and symptoms; oral lesions; abnormal liver function tests; bacterial infections; edema and swelling; viral infections.

Laboratory Abnormalities: There were no clinically relevant changes in these trials. Specifically, no increased reporting of neutrophilia or changes in glucose or potassium was noted.

6.3 Postmarketing Experience

In addition to adverse events reported from clinical trials, the following events have been identified during worldwide use of any formulation of ADVAIR, fluticasone propionate, and/or salmeterol regardless of indication. Because they are reported voluntarily from a population of unknown size, estimates of frequency cannot be made. These events have been chosen for inclusion due to either their seriousness, frequency of reporting, or causal connection to ADVAIR DISKUS, fluticasone propionate, and/or salmeterol or a combination of these factors.

Cardiac Disorders: Arrhythmias (including atrial fibrillation, extrasystoles, supraventricular tachycardia), ventricular tachycardia.

Endocrine Disorders: Cushing’s syndrome, Cushingoid features, growth velocity reduction in children/adolescents, hypercorticism.

Eye Disorders: Glaucoma.

Gastrointestinal Disorders: Abdominal pain, dyspepsia, xerostomia.

Immune System Disorders: Immediate and delayed hypersensitivity reaction (including very rare anaphylactic reaction). Very rare anaphylactic reaction in patients with severe milk protein allergy.

Metabolic and Nutrition Disorders: Hyperglycemia, weight gain.

Musculoskeletal, Connective Tissue, and Bone Disorders: Arthralgia, cramps, myositis, osteoporosis.

Nervous System Disorders: Paresthesia, restlessness.

Psychiatric Disorders: Agitation, aggression, depression. Behavioral changes, including hyperactivity and irritability, have been reported very rarely and primarily in children.

Reproductive System and Breast Disorders: Dysmenorrhea.

Respiratory, Thoracic, and Mediastinal Disorders: Chest congestion; chest tightness; dyspnea; facial and oropharyngeal edema, immediate bronchospasm; paradoxical bronchospasm; tracheitis; wheezing; reports of upper respiratory symptoms of laryngeal spasm, irritation, or swelling such as stridor or choking.

Skin and Subcutaneous Tissue Disorders: Ecchymoses, photodermatitis.

Vascular Disorders: Pallor.

7 DRUG INTERACTIONS

ADVAIR DISKUS has been used concomitantly with other drugs, including short-acting beta2-agonists, methylxanthines, and intranasal corticosteroids, commonly used in patients with asthma or COPD, without adverse drug reactions. No formal drug interaction studies have been performed with ADVAIR DISKUS.

7.1 Inhibitors of Cytochrome P450 3A4

Fluticasone propionate and salmeterol, the individual components of ADVAIR DISKUS, are substrates of CYP3A4. The use of strong CYP3A4 inhibitors (e.g., ritonavir, atazanavir, clarithromycin, indinavir, itraconazole, nefazodone, nelfinavir, saquinavir, ketoconazole, telithromycin) with ADVAIR DISKUS is not recommended because increased systemic corticosteroid and increased cardiovascular adverse effects may occur.

Ritonavir: Fluticasone Propionate: A drug interaction study with fluticasone propionate aqueous nasal spray in healthy subjects has shown that ritonavir (a strong CYP3A4 inhibitor) can significantly increase plasma fluticasone propionate exposure, resulting in significantly reduced serum cortisol concentrations [see Clinical Pharmacology (12.3)]. During postmarketing use, there have been reports of clinically significant drug interactions in patients receiving fluticasone propionate and ritonavir, resulting in systemic corticosteroid effects including Cushing’s syndrome and adrenal suppression.

Ketoconazole: Fluticasone Propionate: Coadministration of orally inhaled fluticasone propionate (1,000 mcg) and ketoconazole (200 mg once daily) resulted in increased plasma fluticasone propionate exposure and reduced plasma cortisol area under the curve (AUC), but had no effect on urinary excretion of cortisol.

Salmeterol: In a drug interaction study in 20 healthy subjects, coadministration of inhaled salmeterol (50 mcg twice daily) and oral ketoconazole (400 mg once daily) for 7 days resulted in greater systemic exposure to salmeterol (AUC increased 16-fold and Cmax increased 1.4-fold). Three (3) subjects were withdrawn due to beta2-agonist side effects (2 with prolonged QTc and 1 with palpitations and sinus tachycardia). Although there was no statistical effect on the mean QTc, coadministration of salmeterol and ketoconazole was associated with more frequent increases in QTc duration compared with salmeterol and placebo administration.

7.2 Monoamine Oxidase Inhibitors and Tricyclic Antidepressants

ADVAIR DISKUS should be administered with extreme caution to patients being treated with monoamine oxidase inhibitors or tricyclic antidepressants, or within 2 weeks of discontinuation of such agents, because the action of salmeterol, a component of ADVAIR DISKUS, on the vascular system may be potentiated by these agents.

7.3 Beta-Adrenergic Receptor Blocking Agents

Beta-blockers not only block the pulmonary effect of beta-agonists, such as salmeterol, a component of ADVAIR DISKUS, but may also produce severe bronchospasm in patients with reversible obstructive airways disease. Therefore, patients with asthma or COPD should not normally be treated with beta-blockers. However, under certain circumstances, there may be no acceptable alternatives to the use of beta-adrenergic blocking agents for these patients; cardioselective beta-blockers could be considered, although they should be administered with caution.

7.4 Diuretics

The ECG changes and/or hypokalemia that may result from the administration of nonpotassium-sparing diuretics (such as loop or thiazide diuretics) can be acutely worsened by beta-agonists, especially when the recommended dose of the beta-agonist is exceeded. Although the clinical relevance of these effects is not known, caution is advised in the coadministration of beta-agonists with nonpotassium-sparing diuretics.

8 USE IN SPECIFIC POPULATIONS

8.1 Pregnancy

Teratogenic Effects: Pregnancy Category C. There are no adequate and well-controlled studies with ADVAIR DISKUS in pregnant women. ADVAIR DISKUS was teratogenic in mice and not in rats, although it lowered fetal weight in rats. Fluticasone propionate alone was teratogenic in mice, rats, and rabbits, and salmeterol alone was teratogenic in rabbits and not in rats. From the reproduction toxicity studies in mice and rats, no evidence of enhanced toxicity was seen using combinations of fluticasone propionate and salmeterol when compared with toxicity data from the components administered separately.

ADVAIR DISKUS should be used during pregnancy only if the potential benefit justifies the potential risk to the fetus.

ADVAIR DISKUS: In the mouse reproduction assay, fluticasone propionate by the subcutaneous route at a dose approximately 3/5 the maximum recommended human daily inhalation dose (MRHD) on an mg/m^2 basis combined with oral salmeterol at a dose approximately 410 times the MRHD on an mg/m^2 basis produced cleft palate, fetal death, increased implantation loss, and delayed ossification. These observations are characteristic of glucocorticoids. No developmental toxicity was observed at combination doses of fluticasone propionate subcutaneously up to approximately 1/6 the MRHD on an mg/m^2 basis and oral doses of salmeterol up to approximately 55 times the MRHD on an mg/m^2 basis. In rats, combining fluticasone propionate subcutaneously at a dose equivalent to the MRHD on an mg/m^2 basis and an oral dose of salmeterol at approximately 810 times the MRHD on an mg/m^2 basis produced decreased fetal weight, umbilical hernia, delayed ossification, and changes in the occipital bone. No such effects were seen when combining fluticasone propionate subcutaneously at a dose less than the MRHD on an mg/m^2 basis and an oral dose of salmeterol at approximately 80 times the MRHD on an mg/m^2 basis.

Fluticasone Propionate: Subcutaneous studies in mice at a dose less than the MRHD on an mg/m^2 basis and in rats at a dose equivalent to the MRHD on an mg/m^2 basis revealed fetal toxicity characteristic of potent corticosteroid compounds, including embryonic growth retardation, omphalocele, cleft palate, and retarded cranial ossification.

In rabbits, fetal weight reduction and cleft palate were observed at a subcutaneous dose less than the MRHD on an mg/m^2 basis. However, no teratogenic effects were reported at oral doses up to approximately 5 times the MRHD on an mg/m^2 basis. No fluticasone propionate was detected in the plasma in this study, consistent with the established low bioavailability following oral administration [see Clinical Pharmacology (12.3)].

Experience with oral corticosteroids since their introduction in pharmacologic, as opposed to physiologic, doses suggests that rodents are more prone to teratogenic effects from corticosteroids than humans. In addition, because there is a natural increase in corticosteroid production during pregnancy, most women will require a lower exogenous corticosteroid dose and many will not need corticosteroid treatment during pregnancy.

Salmeterol: No teratogenic effects occurred in rats at oral doses approximately 160 times the MRHD on an mg/m^2 basis. In pregnant Dutch rabbits administered oral doses approximately 50 times the MRHD based on comparison of the AUCs, salmeterol exhibited fetal toxic effects characteristically resulting from beta-adrenoceptor stimulation. These included precocious eyelid openings, cleft palate, sternebral fusion, limb and paw flexures, and delayed ossification of the frontal cranial bones. No such effects occurred at an oral dose approximately 20 times the MRHD based on comparison of the AUCs.

New Zealand White rabbits were less sensitive since only delayed ossification of the frontal cranial bones was seen at an oral dose approximately 1,600 times the MRHD on an mg/m^2 basis. Extensive use of other beta-agonists has provided no evidence that these class effects in animals are relevant to their use in humans.

8.2 Labor and Delivery

There are no well-controlled human studies that have investigated effects of ADVAIR DISKUS on preterm labor or labor at term. Because of the potential for beta-agonist interference with uterine contractility, use of ADVAIR DISKUS during labor should be restricted to those patients in whom the benefits clearly outweigh the risks.

8.3 Nursing Mothers

Plasma levels of salmeterol, a component of ADVAIR DISKUS, after inhaled therapeutic doses are very low. In rats, salmeterol xinafoate is excreted in the milk. There are no data from controlled trials on the use of salmeterol by nursing mothers. It is not known whether fluticasone propionate, a component of ADVAIR DISKUS, is excreted in human breast milk. However, other corticosteroids have been detected in human milk. Subcutaneous administration to lactating rats of tritiated fluticasone propionate resulted in measurable radioactivity in milk.

Since there are no data from controlled trials on the use of ADVAIR DISKUS by nursing mothers, a decision should be made whether to discontinue nursing or to discontinue ADVAIR DISKUS, taking into account the importance of ADVAIR DISKUS to the mother.

Caution should be exercised when ADVAIR DISKUS is administered to a nursing woman.

8.4 Pediatric Use

Use of ADVAIR DISKUS 100/50 in patients aged 4 to 11 years is supported by extrapolation of efficacy data from older patients and by safety and efficacy data from a study of ADVAIR DISKUS 100/50 in children with asthma aged 4 to 11 years [see Adverse Reactions (6.1), Clinical Studies (14.1)]. The safety and effectiveness of ADVAIR DISKUS in children with asthma less than 4 years of age have not been established.

Inhaled corticosteroids, including fluticasone propionate, a component of ADVAIR DISKUS, may cause a reduction in growth velocity in children and adolescents [see Warnings and Precautions (5.14)]. The growth of pediatric patients receiving orally inhaled corticosteroids, including ADVAIR DISKUS, should be monitored.

A 52-week placebo-controlled study to assess the potential growth effects of fluticasone propionate inhalation powder (FLOVENT® ROTADISK®) at 50 and 100 mcg twice daily was conducted in the US in 325 prepubescent children (244 males and 81 females) aged 4 to 11 years. The mean growth velocities at 52 weeks observed in the intent-to-treat population were 6.32 cm/year in the placebo group (N = 76), 6.07 cm/year in the 50-mcg group (N = 98), and 5.66 cm/year in the 100-mcg group (N = 89). An imbalance in the proportion of children entering puberty between groups and a higher dropout rate in the placebo group due to poorly controlled asthma may be confounding factors in interpreting these data. A separate subset analysis of children who remained prepubertal during the study revealed growth rates at 52 weeks of 6.10 cm/year in the placebo group (n = 57), 5.91 cm/year in the 50-mcg group (n = 74), and 5.67 cm/year in the 100-mcg group (n = 79). In children aged 8.5 years, the mean age of children in this study, the range for expected growth velocity is: boys – 3rd percentile = 3.8 cm/year, 50th percentile = 5.4 cm/year, and 97th percentile = 7.0 cm/year; girls – 3rd percentile = 4.2 cm/year, 50th percentile = 5.7 cm/year, and 97th percentile = 7.3 cm/year. The clinical relevance of these growth data is not certain.

If a child or adolescent on any corticosteroid appears to have growth suppression, the possibility that he/she is particularly sensitive to this effect of corticosteroids should be considered. The potential growth effects of prolonged treatment should be weighed against the clinical benefits obtained. To minimize the systemic effects of orally inhaled corticosteroids, including ADVAIR DISKUS, each patient should be titrated to the lowest strength that effectively controls his/her asthma [see Dosage and Administration (2.1)].

8.5 Geriatric Use

Clinical studies of ADVAIR DISKUS for asthma did not include sufficient numbers of patients aged 65 years and older to determine whether older patients with asthma respond differently than younger patients.

Of the total number of patients in clinical studies receiving ADVAIR DISKUS for COPD, 1,621 were aged 65 years or older and 379 were aged 75 years or older. Patients with COPD aged 65 years and older had a higher incidence of serious adverse events compared with patients less than 65 years of age. Although the distribution of adverse events was similar in the 2 age-groups, patients over 65 years of age experienced more severe events. In two 1-year studies, the excess risk of pneumonia that was seen in patients treated with ADVAIR DISKUS compared with those treated with salmeterol was greater in patients over 65 years of age than in patients less than 65 years of age [see Adverse Reactions (6.2)]. As with other products containing beta2-agonists, special caution should be observed when using ADVAIR DISKUS in geriatric patients who have concomitant cardiovascular disease that could be adversely affected by beta2-agonists. Based on available data for ADVAIR DISKUS or its active components, no adjustment of dosage of ADVAIR DISKUS in geriatric patients is warranted.

No relationship between fluticasone propionate systemic exposure and age was observed in 57 patients with COPD (aged 40 to 82 years) given 250 or 500 mcg twice daily.

8.6 Hepatic Impairment

Formal pharmacokinetic studies using ADVAIR DISKUS have not been conducted in patients with hepatic impairment. However, since both fluticasone propionate and salmeterol are predominantly cleared by hepatic metabolism, impairment of liver function may lead to accumulation of fluticasone propionate and salmeterol in plasma. Therefore, patients with hepatic disease should be closely monitored.

8.7 Renal Impairment

Formal pharmacokinetic studies using ADVAIR DISKUS have not been conducted in patients with renal impairment.

10 OVERDOSAGE

No human overdosage data has been reported for ADVAIR DISKUS.

No deaths occurred in rats given an inhaled single-dose combination of salmeterol 3.6 mg/kg (approximately 290 and 140 times the MRHD for adults and children, respectively, on an mg/m^2 basis) and 1.9 mg/kg of fluticasone propionate (approximately 15 and 35 times the MRHD for adults and children, respectively, on an mg/m^2 basis).

Fluticasone Propionate: Chronic overdosage with fluticasone propionate may result in signs/symptoms of hypercorticism [see Warnings and Precautions (5.7)]. Inhalation by healthy volunteers of a single dose of 4,000 mcg of fluticasone propionate inhalation powder or single doses of 1,760 or 3,520 mcg of fluticasone propionate CFC inhalation aerosol was well tolerated. Fluticasone propionate given by inhalation aerosol at dosages of 1,320 mcg twice daily for 7 to 15 days to healthy human volunteers was also well tolerated. Repeat oral doses up to 80 mg daily for 10 days in healthy volunteers and repeat oral doses up to 20 mg daily for 42 days in patients were well tolerated. Adverse reactions were of mild or moderate severity, and incidences were similar in active and placebo treatment groups.

No deaths were seen in mice given an oral dose of 1,000 mg/kg (4,100 and 9,600 times the MRHD dose for adults and children, respectively, on an mg/m^2 basis). No deaths were seen in rats given an oral dose of 1,000 mg/kg (8,100 and 19,200 times the MRHD for adults and children, respectively, on an mg/m^2 basis).

Salmeterol: The expected signs and symptoms with overdosage of salmeterol are those of excessive beta-adrenergic stimulation and/or occurrence or exaggeration of any of the following: seizures, angina, hypertension or hypotension, tachycardia with rates up to 200 beats/min, arrhythmias, nervousness, headache, tremor, muscle cramps, dry mouth, palpitation, nausea, dizziness, fatigue, malaise, and insomnia. Overdosage with salmeterol can lead to clinically significant prolongation of the QTc interval, which can produce ventricular arrhythmias. Other signs of overdosage may include hypokalemia and hyperglycemia.

As with all sympathomimetic medications, cardiac arrest and even death may be associated with abuse of salmeterol.

Treatment consists of discontinuation of salmeterol together with appropriate symptomatic therapy. The judicious use of a cardioselective beta-receptor blocker may be considered, bearing in mind that such medication can produce bronchospasm. There is insufficient evidence to determine if dialysis is beneficial for overdosage of salmeterol. Cardiac monitoring is recommended in cases of overdosage.

No deaths were seen in rats given salmeterol at an inhalation dose of 2.9 mg/kg (approximately 240 and 110 times the MRHD for adults and children, respectively, on an mg/m^2 basis) and in dogs at an inhalation dose of 0.7 mg/kg (approximately 190 and 90 times the MRHD for adults and children, respectively, on an mg/m^2 basis). By the oral route, no deaths occurred in mice at 150 mg/kg (approximately 6,100 and 2,900 times the MRHD for adults and children, respectively, on an mg/m^2 basis) and in rats at 1,000 mg/kg (approximately 81,000 and 38,000 times the MRHD for adults and children, respectively, on an mg/m^2 basis).

11 DESCRIPTION

ADVAIR DISKUS 100/50, ADVAIR DISKUS 250/50, and ADVAIR DISKUS 500/50 are combinations of fluticasone propionate and salmeterol xinafoate.

One active component of ADVAIR DISKUS is fluticasone propionate, a corticosteroid having the chemical name S-(fluoromethyl) 6α,9-difluoro-11β,17-dihydroxy-16α-methyl-3-oxoandrosta-1,4-diene-17β-carbothioate, 17-propionate and the following chemical structure:

Fluticasone propionate is a white powder with a molecular weight of 500.6, and the empirical formula is C25H31F3O5S. It is practically insoluble in water, freely soluble in dimethyl sulfoxide and dimethylformamide, and slightly soluble in methanol and 95% ethanol.

The other active component of ADVAIR DISKUS is salmeterol xinafoate, a beta2-adrenergic bronchodilator. Salmeterol xinafoate is the racemic form of the 1-hydroxy-2-naphthoic acid salt of salmeterol. The chemical name of salmeterol xinafoate is 4-hydroxy-α^1-[[[6-(4-phenylbutoxy)hexyl]amino]methyl]-1,3-benzenedimethanol, 1-hydroxy-2-naphthalenecarboxylate, and it has the following chemical structure:

Salmeterol xinafoate is a white powder with a molecular weight of 603.8, and the empirical formula is C25H37NO4•C11H8O3. It is freely soluble in methanol; slightly soluble in ethanol, chloroform, and isopropanol; and sparingly soluble in water.

ADVAIR DISKUS 100/50, ADVAIR DISKUS 250/50, and ADVAIR DISKUS 500/50 are specially designed plastic devices containing a double-foil blister strip of a powder formulation of fluticasone propionate and salmeterol xinafoate intended for oral inhalation only. Each blister on the double-foil strip within the device contains 100, 250, or 500 mcg of microfine fluticasone propionate and 72.5 mcg of microfine salmeterol xinafoate salt, equivalent to 50 mcg of salmeterol base, in 12.5 mg of formulation containing lactose (which contains milk proteins). Each blister contains 1 complete dose of both medications. After a blister containing medication is opened by activating the device, the medication is dispersed into the airstream created by the patient inhaling through the mouthpiece.

Under standardized in vitro test conditions, ADVAIR DISKUS delivers 93, 233, and 465 mcg of fluticasone propionate and 45 mcg of salmeterol base per blister from ADVAIR DISKUS 100/50, 250/50, and 500/50, respectively, when tested at a flow rate of 60 L/min for 2 seconds. In adult patients with obstructive lung disease and severely compromised lung function (mean FEV1 20% to 30% of predicted), mean peak inspiratory flow (PIF) through a DISKUS® inhalation device was 82.4 L/min (range: 46.1 to 115.3 L/min).

Inhalation profiles for adolescent (N = 13, aged 12 to 17 years) and adult (N = 17, aged 18 to 50 years) patients with asthma inhaling maximally through the DISKUS device show mean PIF of 122.2 L/min (range: 81.6 to 152.1 L/min). Inhalation profiles for pediatric patients with asthma inhaling maximally through the DISKUS device show a mean PIF of 75.5 L/min (range: 49.0 to 104.8 L/min) for the 4-year-old patient set (N = 20) and 107.3 L/min (range: 82.8 to 125.6 L/min) for the 8-year-old patient set (N = 20).

The actual amount of drug delivered to the lung will depend on patient factors, such as inspiratory flow profile.

12 CLINICAL PHARMACOLOGY

12.1 Mechanism of Action

ADVAIR DISKUS: Since ADVAIR DISKUS contains both fluticasone propionate and salmeterol, the mechanisms of action described below for the individual components apply to ADVAIR DISKUS. These drugs represent 2 classes of medications (a synthetic corticosteroid and a selective LABA) that have different effects on clinical and physiological indices.

Fluticasone Propionate: Fluticasone propionate is a synthetic trifluorinated corticosteroid with potent anti-inflammatory activity. In vitro assays using human lung cytosol preparations have established fluticasone propionate as a human glucocorticoid receptor agonist with an affinity 18 times greater than dexamethasone, almost twice that of beclomethasone-17-monopropionate (BMP), the active metabolite of beclomethasone dipropionate, and over 3 times that of budesonide. Data from the McKenzie vasoconstrictor assay in man are consistent with these results.

Inflammation is an important component in the pathogenesis of asthma. Corticosteroids have been shown to inhibit multiple cell types (e.g., mast cells, eosinophils, basophils, lymphocytes, macrophages, neutrophils) and mediator production or secretion (e.g., histamine, eicosanoids, leukotrienes, cytokines) involved in the asthmatic response. These anti-inflammatory actions of corticosteroids contribute to their efficacy in asthma.

Inflammation is also a component in the pathogenesis of COPD. In contrast to asthma, however, the predominant inflammatory cells in COPD include neutrophils, CD8+ T-lymphocytes, and macrophages. The effects of corticosteroids in the treatment of COPD are not well defined and inhaled corticosteroids and fluticasone propionate when used apart from ADVAIR DISKUS are not indicated for the treatment of COPD.

Salmeterol Xinafoate: Salmeterol is a selective LABA. In vitro studies show salmeterol to be at least 50 times more selective for beta2-adrenoceptors than albuterol. Although beta2-adrenoceptors are the predominant adrenergic receptors in bronchial smooth muscle and beta1-adrenoceptors are the predominant receptors in the heart, there are also beta2-adrenoceptors in the human heart comprising 10% to 50% of the total beta-adrenoceptors. The precise function of these receptors has not been established, but their presence raises the possibility that even highly selective beta2-agonists may have cardiac effects.

The pharmacologic effects of beta2-adrenoceptor agonist drugs, including salmeterol, are at least in part attributable to stimulation of intracellular adenyl cyclase, the enzyme that catalyzes the conversion of adenosine triphosphate (ATP) to cyclic-3′,5′-adenosine monophosphate (cyclic AMP). Increased cyclic AMP levels cause relaxation of bronchial smooth muscle and inhibition of release of mediators of immediate hypersensitivity from cells, especially from mast cells.

In vitro tests show that salmeterol is a potent and long-lasting inhibitor of the release of mast cell mediators, such as histamine, leukotrienes, and prostaglandin D2, from human lung. Salmeterol inhibits histamine-induced plasma protein extravasation and inhibits platelet-activating factor-induced eosinophil accumulation in the lungs of guinea pigs when administered by the inhaled route. In humans, single doses of salmeterol administered via inhalation aerosol attenuate allergen-induced bronchial hyper-responsiveness.

12.2 Pharmacodynamics

ADVAIR DISKUS: Healthy Subjects: Cardiovascular Effects: Since systemic pharmacodynamic effects of salmeterol are not normally seen at the therapeutic dose, higher doses were used to produce measurable effects. Four (4) studies were conducted in healthy adult subjects: (1) a single-dose crossover study using 2 inhalations of ADVAIR DISKUS 500/50, fluticasone propionate powder 500 mcg and salmeterol powder 50 mcg given concurrently, or fluticasone propionate powder 500 mcg given alone, (2) a cumulative dose study using 50 to 400 mcg of salmeterol powder given alone or as ADVAIR DISKUS 500/50, (3) a repeat-dose study for 11 days using 2 inhalations twice daily of ADVAIR DISKUS 250/50, fluticasone propionate powder 250 mcg, or salmeterol powder 50 mcg, and (4) a single-dose study using 5 inhalations of ADVAIR DISKUS 100/50, fluticasone propionate powder 100 mcg alone, or placebo. In these studies no significant differences were observed in the pharmacodynamic effects of salmeterol (pulse rate, blood pressure, QTc interval, potassium, and glucose) whether the salmeterol was given as ADVAIR DISKUS, concurrently with fluticasone propionate from separate inhalers, or as salmeterol alone. The systemic pharmacodynamic effects of salmeterol were not altered by the presence of fluticasone propionate in ADVAIR DISKUS. The potential effect of salmeterol on the effects of fluticasone propionate on the HPA axis was also evaluated in these studies.

HPA Axis Effects: No significant differences across treatments were observed in 24-hour urinary cortisol excretion and, where measured, 24-hour plasma cortisol AUC. The systemic pharmacodynamic effects of fluticasone propionate were not altered by the presence of salmeterol in ADVAIR DISKUS in healthy subjects.

Asthma: Adult and Adolescent Patients: Cardiovascular Effects: In clinical studies with ADVAIR DISKUS in adult and adolescent patients aged 12 years and older with asthma, no significant differences were observed in the systemic pharmacodynamic effects of salmeterol (pulse rate, blood pressure, QTc interval, potassium, and glucose) whether the salmeterol was given alone or as ADVAIR DISKUS. In 72 adult and adolescent patients with asthma given either ADVAIR DISKUS 100/50 or ADVAIR DISKUS 250/50, continuous 24-hour electrocardiographic monitoring was performed after the first dose and after 12 weeks of therapy, and no clinically significant dysrhythmias were noted.

HPA Axis Effects: In a 28-week study in adult and adolescent patients with asthma, ADVAIR DISKUS 500/50 twice daily was compared with the concurrent use of salmeterol powder 50 mcg plus fluticasone propionate powder 500 mcg from separate inhalers or fluticasone propionate powder 500 mcg alone. No significant differences across treatments were observed in serum cortisol AUC after 12 weeks of dosing or in 24-hour urinary cortisol excretion after 12 and 28 weeks.

In a 12-week study in adult and adolescent patients with asthma, ADVAIR DISKUS 250/50 twice daily was compared with fluticasone propionate powder 250 mcg alone, salmeterol powder 50 mcg alone, and placebo. For most patients, the ability to increase cortisol production in response to stress, as assessed by 30-minute cosyntropin stimulation, remained intact with ADVAIR DISKUS. One patient (3%) who received ADVAIR DISKUS 250/50 had an abnormal response (peak serum cortisol <18 mcg/dL) after dosing, compared with 2 patients (6%) who received placebo, 2 patients (6%) who received fluticasone propionate 250 mcg, and no patients who received salmeterol.

In a repeat-dose, 3-way crossover study, 1 inhalation twice daily of ADVAIR DISKUS 100/50, FLOVENT® DISKUS® 100 mcg (fluticasone propionate inhalation powder, 100 mcg), or placebo was administered to 20 adult and adolescent patients with asthma. After 28 days of treatment, geometric mean serum cortisol AUC over 12 hours showed no significant difference between ADVAIR DISKUS and FLOVENT DISKUS or between either active treatment and placebo.

Pediatric Patients: HPA Axis Effects: In a 12-week study in patients with asthma aged 4 to 11 years who were receiving inhaled corticosteroids at study entry, ADVAIR DISKUS 100/50 twice daily was compared with fluticasone propionate inhalation powder 100 mcg administered twice daily via the DISKUS. The values for 24-hour urinary cortisol excretion at study entry and after 12 weeks of treatment were similar within each treatment group. After 12 weeks, 24-hour urinary cortisol excretion was also similar between the 2 groups.

Chronic Obstructive Pulmonary Disease: Cardiovascular Effects:In clinical studies with ADVAIR DISKUS in patients with COPD, no significant differences were seen in pulse rate, blood pressure, potassium, and glucose between ADVAIR DISKUS, the individual components of ADVAIR DISKUS, and placebo. In a study of ADVAIR DISKUS 250/50, 8 patients (2 [1.1%] in the group given ADVAIR DISKUS 250/50, 1 [0.5%] in the fluticasone propionate 250-mcg group, 3 [1.7%] in the salmeterol group, and 2 [1.1%] in the placebo group) had QTc intervals >470 msec at least 1 time during the treatment period. Five (5) of these 8 patients had a prolonged QTc interval at baseline.

In a 24-week study, 130 patients with COPD received continuous 24-hour electrocardiographic monitoring prior to the first dose and after 4 weeks of twice-daily treatment with either ADVAIR DISKUS 500/50, fluticasone propionate powder 500 mcg, salmeterol powder 50 mcg, or placebo. No significant differences in ventricular or supraventricular arrhythmias and heart rate were observed among the groups treated with ADVAIR DISKUS 500/50, the individual components, or placebo. One (1) subject in the fluticasone propionate group experienced atrial flutter/atrial fibrillation, and 1 subject in the group given ADVAIR DISKUS 500/50 experienced heart block. There were 3 cases of nonsustained ventricular tachycardia (1 each in the placebo, salmeterol, and fluticasone propionate 500-mcg treatment groups).

In 24-week clinical studies in patients with COPD, the incidence of clinically significant ECG abnormalities (myocardial ischemia, ventricular hypertrophy, clinically significant conduction abnormalities, clinically significant arrhythmias) was lower for patients who received salmeterol (1%, 9 of 688 patients who received either salmeterol 50 mcg or ADVAIR DISKUS) compared with placebo (3%, 10 of 370 patients).

No significant differences with salmeterol 50 mcg alone or in combination with fluticasone propionate as ADVAIR DISKUS 500/50 were observed on pulse rate and systolic and diastolic blood pressure in a subset of patients with COPD who underwent 12-hour serial vital sign measurements after the first dose (N = 183) and after 12 weeks of therapy (N = 149). Median changes from baseline in pulse rate and systolic and diastolic blood pressure were similar to those seen with placebo.

HPA Axis Effects: Short-cosyntropin stimulation testing was performed both at Day 1 and Endpoint in 101 patients with COPD receiving twice-daily ADVAIR DISKUS 250/50, fluticasone propionate powder 250 mcg, salmeterol powder 50 mcg, or placebo. For most patients, the ability to increase cortisol production in response to stress, as assessed by short cosyntropin stimulation, remained intact with ADVAIR DISKUS 250/50. One (1) patient (3%) who received ADVAIR DISKUS 250/50 had an abnormal stimulated cortisol response (peak cortisol <14.5 mcg/dL assessed by high-performance liquid chromatography) after dosing, compared with 2 patients (9%) who received fluticasone propionate 250 mcg, 2 patients (7%) who received salmeterol 50 mcg, and 1 patient (4%) who received placebo following 24 weeks of treatment or early discontinuation from study.

After 36 weeks of dosing, serum cortisol concentrations in a subset of patients with COPD (n = 83) were 22% lower in patients receiving ADVAIR DISKUS 500/50 and 21% lower in patients receiving fluticasone propionate 500 mcg than in patients receiving placebo.

Other Fluticasone Propionate Products: Asthma: HPA Axis Effects: In clinical trials with fluticasone propionate inhalation powder using doses up to and including 250 mcg twice daily, occasional abnormal short cosyntropin tests (peak serum cortisol <18 mcg/dL assessed by radioimmunoassay) were noted both in patients receiving fluticasone propionate and in patients receiving placebo. The incidence of abnormal tests at 500 mcg twice daily was greater than placebo. In a 2-year study carried out with the DISKHALER® inhalation device in 64 patients with mild, persistent asthma (mean FEV1 91% of predicted) randomized to fluticasone propionate 500 mcg twice daily or placebo, no patient receiving fluticasone propionate had an abnormal response to 6-hour cosyntropin infusion (peak serum cortisol <18 mcg/dL). With a peak cortisol threshold of <35 mcg/dL, 1 patient receiving fluticasone propionate (4%) had an abnormal response at 1 year; repeat testing at 18 months and 2 years was normal. Another patient receiving fluticasone propionate (5%) had an abnormal response at 2 years. No patient on placebo had an abnormal response at 1 or 2 years.

Chronic Obstructive Pulmonary Disease: HPA Axis Effects: After 4 weeks of dosing, the steady-state fluticasone propionate pharmacokinetics and serum cortisol levels were described in a subset of patients with COPD (n = 86) randomized to twice-daily fluticasone propionate inhalation powder via the DISKUS 500 mcg, fluticasone propionate inhalation powder 250 mcg, or placebo. Serial serum cortisol concentrations were measured across a 12-hour dosing interval. Serum cortisol concentrations following 250- and 500-mcg twice-daily dosing were 10% and 21% lower than placebo, respectively, indicating a dose-dependent increase in systemic exposure to fluticasone propionate.

Other Salmeterol Xinafoate Products: Asthma: Cardiovascular Effects: Inhaled salmeterol, like other beta-adrenergic agonist drugs, can produce dose-related cardiovascular effects and effects on blood glucose and/or serum potassium [see Warnings and Precautions (5.12, 5.18)]. The cardiovascular effects (heart rate, blood pressure) associated with salmeterol occur with similar frequency, and are of similar type and severity, as those noted following albuterol administration.

The effects of rising doses of inhaled salmeterol and standard inhaled doses of albuterol were studied in volunteers and in patients with asthma. Salmeterol doses up to 84 mcg administered as inhalation aerosol resulted in heart rate increases of 3 to 16 beats/min, about the same as albuterol dosed at 180 mcg by inhalation aerosol (4 to 10 beats/min). Adolescent and adult patients receiving 50-mcg doses of salmeterol inhalation powder (N = 60) underwent continuous electrocardiographic monitoring during two 12-hour periods after the first dose and after 1 month of therapy, and no clinically significant dysrhythmias were noted.

Concomitant Use of ADVAIR DISKUS With Other Respiratory Medications: Short-Acting Beta2-Agonists: In clinical trials with patients with asthma, the mean daily need for albuterol by 166 adult and adolescent patients aged 12 years and older using ADVAIR DISKUS was approximately 1.3 inhalations/day and ranged from 0 to 9 inhalations/day. Five percent (5%) of patients using ADVAIR DISKUS in these trials averaged 6 or more inhalations per day over the course of the 12-week trials. No increase in frequency of cardiovascular adverse reactions was observed among patients who averaged 6 or more inhalations per day.

In a COPD clinical trial, the mean daily need for albuterol for patients using ADVAIR DISKUS 250/50 was 4.1 inhalations/day. Twenty-six percent (26%) of patients using ADVAIR DISKUS 250/50 averaged 6 or more inhalations per day over the course of the 24-week trial. No increase in frequency of cardiovascular adverse reactions was observed among patients who averaged 6 or more inhalations of albuterol per day.

Methylxanthines: The concurrent use of intravenously or orally administered methylxanthines (e.g., aminophylline, theophylline) by adult and adolescent patients aged 12 years and older receiving ADVAIR DISKUS has not been completely evaluated. In clinical trials with patients with asthma, 39 patients receiving ADVAIR DISKUS 100/50, 250/50, or 500/50 twice daily concurrently with a theophylline product had adverse event rates similar to those in 304 patients receiving ADVAIR DISKUS without theophylline. Similar results were observed in patients receiving salmeterol 50 mcg plus fluticasone propionate 500 mcg twice daily concurrently with a theophylline product (n = 39) or without theophylline (n = 132).

In a COPD clinical trial, 17 patients receiving ADVAIR DISKUS 250/50 twice daily concurrently with a theophylline product had adverse event rates similar to those in 161 patients receiving ADVAIR DISKUS without theophylline. Based on the available data, the concomitant administration of methylxanthines with ADVAIR DISKUS did not alter the observed adverse event profile.

Fluticasone Propionate Nasal Spray: In adult and adolescent patients aged 12 years and older taking ADVAIR DISKUS in clinical trials, no difference in the profile of adverse events or HPA axis effects was noted between patients who were taking FLONASE® (fluticasone propionate) Nasal Spray, 50 mcg concurrently (n = 46) and those who were not (n = 130).

12.3 Pharmacokinetics

Absorption: Fluticasone Propionate: Healthy Subjects: Fluticasone propionate acts locally in the lung; therefore, plasma levels do not predict therapeutic effect. Studies using oral dosing of labeled and unlabeled drug have demonstrated that the oral systemic bioavailability of fluticasone propionate is negligible (<1%), primarily due to incomplete absorption and presystemic metabolism in the gut and liver. In contrast, the majority of the fluticasone propionate delivered to the lung is systemically absorbed.

Following administration of ADVAIR DISKUS to healthy adult subjects, peak plasma concentrations of fluticasone propionate were achieved in 1 to 2 hours. In a single-dose crossover study, a higher-than-recommended dose of ADVAIR DISKUS was administered to 14 healthy adult subjects. Two (2) inhalations of the following treatments were administered: ADVAIR DISKUS 500/50, fluticasone propionate powder 500 mcg and salmeterol powder 50 mcg given concurrently, and fluticasone propionate powder 500 mcg alone. Mean peak plasma concentrations of fluticasone propionate averaged 107, 94, and 120 pg/mL, respectively, indicating no significant changes in systemic exposures of fluticasone propionate.

In 15 healthy subjects, systemic exposure to fluticasone propionate from 4 inhalations of ADVAIR® HFA 230/21 (fluticasone propionate 230 mcg and salmeterol 21 mcg) Inhalation Aerosol (920/84 mcg) and 2 inhalations of ADVAIR DISKUS 500/50 (1,000/100 mcg) were similar between the 2 inhalers (i.e., 799 versus 832 pg•hr/mL, respectively), but approximately half the systemic exposure from 4 inhalations of fluticasone propionate CFC inhalation aerosol 220 mcg (880 mcg, AUC = 1,543 pg•hr/mL). Similar results were observed for peak fluticasone propionate plasma concentrations (186 and 182 pg/mL from ADVAIR HFA and ADVAIR DISKUS, respectively, and 307 pg/mL from the fluticasone propionate CFC inhalation aerosol). Absolute bioavailability of fluticasone propionate was 5.3% and 5.5% following administration of ADVAIR HFA and ADVAIR DISKUS, respectively.

Asthma and COPD Patients: Peak steady-state fluticasone propionate plasma concentrations in adult patients with asthma (N = 11) ranged from undetectable to 266 pg/mL after a 500-mcg twice-daily dose of fluticasone propionate inhalation powder using the DISKUS device. The mean fluticasone propionate plasma concentration was 110 pg/mL.

Full pharmacokinetic profiles were obtained from 9 female and 16 male patients with asthma given fluticasone propionate inhalation powder 500 mcg twice daily using the DISKUS device and from 14 female and 43 male patients with COPD given 250 or 500 mcg twice daily. No overall differences in fluticasone propionate pharmacokinetics were observed.

Peak steady-state fluticasone propionate plasma concentrations in patients with COPD averaged 53 pg/mL (range: 19.3 to 159.3 pg/mL) after treatment with 250 mcg twice daily (N = 30) and 84 pg/mL (range: 24.3 to 197.1 pg/mL) after treatment with 500 mcg twice daily (N = 27) via the fluticasone propionate DISKUS device. In another study in patients with COPD, peak steady-state fluticasone propionate plasma concentrations averaged 115 pg/mL (range: 52.6 to 366.0 pg/mL) after treatment with 500 mcg twice daily via the fluticasone propionate DISKUS device (N = 15) and 105 pg/mL (range: 22.5 to 299.0 pg/mL) via ADVAIR DISKUS (N = 24).

Salmeterol Xinafoate: Healthy Subjects: Salmeterol xinafoate, an ionic salt, dissociates in solution so that the salmeterol and 1-hydroxy-2-naphthoic acid (xinafoate) moieties are absorbed, distributed, metabolized, and eliminated independently. Salmeterol acts locally in the lung; therefore, plasma levels do not predict therapeutic effect.

Following administration of ADVAIR DISKUS to healthy adult subjects, peak plasma concentrations of salmeterol were achieved in about 5 minutes.

In 15 healthy subjects receiving ADVAIR HFA 230/21 Inhalation Aerosol (920/84 mcg) and ADVAIR DISKUS 500/50 (1,000/100 mcg), systemic exposure to salmeterol was higher (317 versus 169 pg•hr/mL) and peak salmeterol concentrations were lower (196 versus 223 pg/mL) following ADVAIR HFA compared with ADVAIR DISKUS, although pharmacodynamic results were comparable.

Asthma Patients: Because of the small therapeutic dose, systemic levels of salmeterol are low or undetectable after inhalation of recommended doses (50 mcg of salmeterol inhalation powder twice daily). Following chronic administration of an inhaled dose of 50 mcg of salmeterol inhalation powder twice daily, salmeterol was detected in plasma within 5 to 45 minutes in 7 patients with asthma; plasma concentrations were very low, with mean peak concentrations of 167 pg/mL at 20 minutes and no accumulation with repeated doses.

Distribution: Fluticasone Propionate: Following intravenous administration, the initial disposition phase for fluticasone propionate was rapid and consistent with its high lipid solubility and tissue binding. The volume of distribution averaged 4.2 L/kg.

The percentage of fluticasone propionate bound to human plasma proteins averages 91%. Fluticasone propionate is weakly and reversibly bound to erythrocytes and is not significantly bound to human transcortin.

Salmeterol: The percentage of salmeterol bound to human plasma proteins averages 96% in vitro over the concentration range of 8 to 7,722 ng of salmeterol base per milliliter, much higher concentrations than those achieved following therapeutic doses of salmeterol.

Metabolism: Fluticasone Propionate: The total clearance of fluticasone propionate is high (average, 1,093 mL/min), with renal clearance accounting for less than 0.02% of the total. The only circulating metabolite detected in man is the 17β-carboxylic acid derivative of fluticasone propionate, which is formed through the CYP3A4 pathway. This metabolite had less affinity (approximately 1/2,000) than the parent drug for the glucocorticoid receptor of human lung cytosol in vitro and negligible pharmacological activity in animal studies. Other metabolites detected in vitro using cultured human hepatoma cells have not been detected in man.

Salmeterol: Salmeterol base is extensively metabolized by hydroxylation, with subsequent elimination predominantly in the feces. No significant amount of unchanged salmeterol base was detected in either urine or feces.

An in vitro study using human liver microsomes showed that salmeterol is extensively metabolized to α-hydroxysalmeterol (aliphatic oxidation) by CYP3A4. Ketoconazole, a strong inhibitor of CYP3A4, essentially completely inhibited the formation of α-hydroxysalmeterol in vitro.

Elimination: Fluticasone Propionate: Following intravenous dosing, fluticasone propionate showed polyexponential kinetics and had a terminal elimination half-life of approximately 7.8 hours. Less than 5% of a radiolabeled oral dose was excreted in the urine as metabolites, with the remainder excreted in the feces as parent drug and metabolites. Terminal half-life estimates of fluticasone propionate for ADVAIR HFA, ADVAIR DISKUS, and fluticasone propionate CFC inhalation aerosol were similar and averaged 5.6 hours.

Salmeterol: In 2 healthy adult subjects who received 1 mg of radiolabeled salmeterol (as salmeterol xinafoate) orally, approximately 25% and 60% of the radiolabeled salmeterol was eliminated in urine and feces, respectively, over a period of 7 days. The terminal elimination half-life was about 5.5 hours (1 volunteer only).

The xinafoate moiety has no apparent pharmacologic activity. The xinafoate moiety is highly protein bound (>99%) and has a long elimination half-life of 11 days. No terminal half-life estimates were calculated for salmeterol following administration of ADVAIR DISKUS.

Special Populations: A population pharmacokinetic analysis was performed for fluticasone propionate and salmeterol utilizing data from 9 controlled clinical trials that included 350 patients with asthma aged 4 to 77 years who received treatment with ADVAIR DISKUS, the combination of HFA-propelled fluticasone propionate and salmeterol inhalation aerosol (ADVAIR HFA), fluticasone propionate inhalation powder (FLOVENT DISKUS), HFA-propelled fluticasone propionate inhalation aerosol (FLOVENT® HFA), or CFC-propelled fluticasone propionate inhalation aerosol. The population pharmacokinetic analyses for fluticasone propionate and salmeterol showed no clinically relevant effects of age, gender, race, body weight, body mass index, or percent of predicted FEV1 on apparent clearance and apparent volume of distribution.

Age: When the population pharmacokinetic analysis for fluticasone propionate was divided into subgroups based on fluticasone propionate strength, formulation, and age (adolescents/adults and children), there were some differences in fluticasone propionate exposure. Higher fluticasone propionate exposure from ADVAIR DISKUS 100/50 compared with FLOVENT DISKUS 100 mcg was observed in adolescents and adults (ratio 1.52 [90% CI: 1.08, 2.13]). However, in clinical studies of up to 12 weeks’ duration comparing ADVAIR DISKUS 100/50 and FLOVENT DISKUS 100 mcg in adolescents and adults, no differences in systemic effects of corticosteroid treatment (e.g., HPA axis effects) were observed. Similar fluticasone propionate exposure was observed from ADVAIR DISKUS 500/50 and FLOVENT DISKUS 500 mcg (ratio 0.83 [90% CI: 0.65, 1.07]) in adolescents and adults.

Steady-state systemic exposure to salmeterol when delivered as ADVAIR DISKUS 100/50, ADVAIR DISKUS 250/50, or ADVAIR HFA 115/21 (fluticasone propionate 115 mcg and salmeterol 21 mcg) Inhalation Aerosol was evaluated in 127 patients aged 4 to 57 years. The geometric mean AUC was 325 pg•hr/mL (90% CI: 309, 341) in adolescents and adults.

The population pharmacokinetic analysis included 160 patients with asthma aged 4 to 11 years who received ADVAIR DISKUS 100/50 or FLOVENT DISKUS 100 mcg. Higher fluticasone propionate exposure (AUC) was observed in children from ADVAIR DISKUS 100/50 compared with FLOVENT DISKUS 100 mcg (ratio 1.20 [90% CI: 1.06, 1.37]). Higher fluticasone propionate exposure (AUC) from ADVAIR DISKUS 100/50 was observed in children compared with adolescents and adults (ratio 1.63 [90% CI: 1.35, 1.96]). However, in clinical studies of up to 12 weeks’ duration comparing ADVAIR DISKUS 100/50 and FLOVENT DISKUS 100 mcg in both adolescents and adults and in children, no differences in systemic effects of corticosteroid treatment (e.g., HPA axis effects) were observed.

Exposure to salmeterol was higher in children compared with adolescents and adults who received ADVAIR DISKUS 100/50 (ratio 1.23 [90% CI: 1.10, 1.38]). However, in clinical studies of up to 12 weeks’ duration with ADVAIR DISKUS 100/50 in both adolescents and adults and in children, no differences in systemic effects of beta2-agonist treatment (e.g., cardiovascular effects, tremor) were observed.

Gender: The population pharmacokinetic analysis involved 202 males and 148 females with asthma who received fluticasone propionate alone or in combination with salmeterol and showed no gender differences for fluticasone propionate pharmacokinetics.

The population pharmacokinetic analysis involved 76 males and 51 females with asthma who received salmeterol in combination with fluticasone propionate and showed no gender differences for salmeterol pharmacokinetics.

Hepatic and Renal Impairment: Formal pharmacokinetic studies using ADVAIR DISKUS have not been conducted in patients with hepatic or renal impairment. However, since both fluticasone propionate and salmeterol are predominantly cleared by hepatic metabolism, impairment of liver function may lead to accumulation of fluticasone propionate and salmeterol in plasma. Therefore, patients with hepatic disease should be closely monitored.

Drug Interactions: In the repeat- and single-dose studies, there was no evidence of significant drug interaction in systemic exposure between fluticasone propionate and salmeterol when given as ADVAIR DISKUS. The population pharmacokinetic analysis from 9 controlled clinical trials in 350 patients with asthma showed no significant effects on fluticasone propionate or salmeterol pharmacokinetics following co-administration with beta2-agonists, corticosteroids, antihistamines, or theophyllines.

Inhibitors of Cytochrome P450 3A4: Ritonavir: Fluticasone Propionate: Fluticasone propionate is a substrate of CYP3A4. Coadministration of fluticasone propionate and the strong CYP3A4 inhibitor ritonavir is not recommended based upon a multiple-dose, crossover drug interaction study in 18 healthy subjects. Fluticasone propionate aqueous nasal spray (200 mcg once daily) was coadministered for 7 days with ritonavir (100 mg twice daily). Plasma fluticasone propionate concentrations following fluticasone propionate aqueous nasal spray alone were undetectable (<10 pg/mL) in most subjects, and when concentrations were detectable peak levels (Cmax) averaged 11.9 pg/mL (range: 10.8 to 14.1 pg/mL) and AUC(0-τ) averaged 8.43 pg•hr/mL (range: 4.2 to 18.8 pg•hr/mL). Fluticasone propionate Cmax and AUC(0-τ) increased to 318 pg/mL (range: 110 to 648 pg/mL) and 3,102.6 pg•hr/mL (range: 1,207.1 to 5,662.0 pg•hr/mL), respectively, after coadministration of ritonavir with fluticasone propionate aqueous nasal spray. This significant increase in plasma fluticasone propionate exposure resulted in a significant decrease (86%) in serum cortisol AUC.

Ketoconazole: Fluticasone Propionate: In a placebo-controlled, crossover study in 8 healthy adult volunteers, coadministration of a single dose of orally inhaled fluticasone propionate (1,000 mcg) with multiple doses of ketoconazole (200 mg) to steady state resulted in increased plasma fluticasone propionate exposure, a reduction in plasma cortisol AUC, and no effect on urinary excretion of cortisol.

Salmeterol: In a placebo-controlled, crossover drug interaction study in 20 healthy male and female subjects, coadministration of salmeterol (50 mcg twice daily) and the strong CYP3A4 inhibitor ketoconazole (400 mg once daily) for 7 days resulted in a significant increase in plasma salmeterol exposure as determined by a 16-fold increase in AUC (ratio with and without ketoconazole 15.76 [90% CI: 10.66, 23.31]) mainly due to increased bioavailability of the swallowed portion of the dose. Peak plasma salmeterol concentrations were increased by 1.4-fold (90% CI: 1.23, 1.68). Three (3) out of 20 subjects (15%) were withdrawn from salmeterol and ketoconazole coadministration due to beta-agonist–mediated systemic effects (2 with QTc prolongation and 1 with palpitations and sinus tachycardia). Coadministration of salmeterol and ketoconazole did not result in a clinically significant effect on mean heart rate, mean blood potassium, or mean blood glucose. Although there was no statistical effect on the mean QTc, coadministration of salmeterol and ketoconazole was associated with more frequent increases in QTc duration compared with salmeterol and placebo administration.

Erythromycin: Fluticasone Propionate: In a multiple-dose drug interaction study, coadministration of orally inhaled fluticasone propionate (500 mcg twice daily) and erythromycin (333 mg 3 times daily) did not affect fluticasone propionate pharmacokinetics.

Salmeterol: In a repeat-dose study in 13 healthy subjects, concomitant administration of erythromycin (a moderate CYP3A4 inhibitor) and salmeterol inhalation aerosol resulted in a 40% increase in salmeterol Cmax at steady state (ratio with and without erythromycin 1.4 [90% CI: 0.96, 2.03], p = 0.12), a 3.6-beat/min increase in heart rate ([95% CI: 0.19, 7.03], p<0.04), a 5.8-msec increase in QTc interval ([95% CI: -6.14, 17.77], p = 0.34), and no change in plasma potassium.

13 NONCLINICAL TOXICOLOGY

13.1 Carcinogenesis, Mutagenesis, Impairment of Fertility

Fluticasone Propionate: Fluticasone propionate demonstrated no tumorigenic potential in mice at oral doses up to 1,000 mcg/kg (approximately 4 and 10 times the MRHD for adults and children, respectively, on an mg/m^2 basis) for 78 weeks or in rats at inhalation doses up to 57 mcg/kg (less than and approximately equivalent to the MRHD for adults and children, respectively, on an mg/m^2 basis) for 104 weeks.

Fluticasone propionate did not induce gene mutation in prokaryotic or eukaryotic cells in vitro. No significant clastogenic effect was seen in cultured human peripheral lymphocytes in vitro or in the in vivo mouse micronucleus test.

No evidence of impairment of fertility was observed in reproductive studies conducted in rats at subcutaneous doses up to 50 mcg/kg (less than the MRHD on an mg/m^2 basis). Prostate weight was significantly reduced.

Salmeterol: In an 18-month carcinogenicity study in CD-mice, salmeterol at oral doses of 1.4 mg/kg and above (approximately 20 times the MRHD for adults and children based on comparison of the plasma AUCs) caused a dose-related increase in the incidence of smooth muscle hyperplasia, cystic glandular hyperplasia, leiomyomas of the uterus, and ovarian cysts. No tumors were seen at 0.2 mg/kg (approximately 3 times the MRHD for adults and children based on comparison of the AUCs).

In a 24-month oral and inhalation carcinogenicity study in Sprague Dawley rats, salmeterol caused a dose-related increase in the incidence of mesovarian leiomyomas and ovarian cysts at doses of 0.68 mg/kg and above (approximately 55 and 25 times the MRHD for adults and children, respectively, on an mg/m^2 basis). No tumors were seen at 0.21 mg/kg (approximately 15 and 8 times the MRHD for adults and children, respectively, on an mg/m^2 basis). These findings in rodents are similar to those reported previously for other beta-adrenergic agonist drugs. The relevance of these findings to human use is unknown.

Salmeterol produced no detectable or reproducible increases in microbial and mammalian gene mutation in vitro. No clastogenic activity occurred in vitro in human lymphocytes or in vivo in a rat micronucleus test. No effects on fertility were identified in rats treated with salmeterol at oral doses up to 2 mg/kg (approximately 160 times the MRHD for adults on an mg/m^2 basis).

13.2 Animal Toxicology and/or Pharmacology

Preclinical: Studies in laboratory animals (minipigs, rodents, and dogs) have demonstrated the occurrence of cardiac arrhythmias and sudden death (with histologic evidence of myocardial necrosis) when beta-agonists and methylxanthines are administered concurrently. The clinical relevance of these findings is unknown.

Reproductive Toxicology Studies: ADVAIR DISKUS: In mice, combining 150 mcg/kg subcutaneously of fluticasone propionate (less than the MRHD on an mg/m^2 basis) with 10 mg/kg orally of salmeterol (approximately 410 times the MRHD on an mg/m^2 basis) produced cleft palate, fetal death, increased implantation loss, and delayed ossification. No such effects were observed at combination subcutaneous doses up to 40 mcg/kg subcutaneously of fluticasone propionate (less than the MRHD on an mg/m^2 basis) and up to 1.4 mg/kg orally doses of salmeterol (approximately 55 times the MRHD on an mg/m^2 basis).

In rats, combining 100 mcg/kg subcutaneously of fluticasone propionate (equivalent to the MRHD on an mg/m^2 basis) and 10 mg/kg orally of salmeterol (approximately 810 times the MRHD on an mg/m^2 basis) produced decreased fetal weight, umbilical hernia, delayed ossification, and changes in the occipital bone. No such effects were observed at combination doses up to 30 mcg/kg subcutaneously of fluticasone propionate (less than the MRHD on an mg/m^2 basis) and up to 1 mg/kg orally of salmeterol (approximately 80 times the MRHD on an mg/m^2 basis).

Fluticasone Propionate: Subcutaneous studies in the mouse and rat at 45 and 100 mcg/kg (less than and equivalent to the MRHD on an mg/m^2 basis), respectively, revealed fetal toxicity characteristic of potent corticosteroid compounds, including embryonic growth retardation, omphalocele, cleft palate, and retarded cranial ossification.

In the rabbit, fetal weight reduction and cleft palate were observed at a subcutaneous dose of 4 mcg/kg (less than the MRHD on an mg/m^2 basis). However, no teratogenic effects were reported at oral doses up to 300 mcg/kg (approximately 5 times the MRHD on an mg/m^2 basis) of fluticasone propionate. No fluticasone propionate was detected in the plasma in this study, consistent with the established low bioavailability following oral administration [see Clinical Pharmacology (12.3)].

Fluticasone propionate crossed the placenta following subcutaneous administration to mice and rats and oral administration to rabbits.

Salmeterol: No teratogenic effects occurred in rats at oral doses up to 2 mg/kg (approximately 160 times the MRHD on an mg/m^2 basis).

In Dutch rabbits administered oral doses of 1 mg/kg and above (approximately 50 times and above the MRHD based on comparison of the AUCs), salmeterol exhibited fetal toxic effects characteristically resulting from beta-adrenoceptor stimulation. These included precocious eyelid openings, cleft palate, sternebral fusion, limb and paw flexures, and delayed ossification of the frontal cranial bones. No such effects occurred at an oral dose of 0.6 mg/kg (approximately 20 times the MRHD based on comparison of the AUCs). New Zealand White rabbits were less sensitive since only delayed ossification of the frontal bones was seen at an oral dose of 10 mg/kg (approximately 1,600 times the MRHD on an mg/m^2 basis).

Salmeterol crossed the placenta following oral administration to mice and rats.

14 CLINICAL STUDIES

14.1 Asthma

Adult and Adolescent Patients Aged 12 Years and Older: In clinical trials comparing ADVAIR DISKUS with its individual components, improvements in most efficacy endpoints were greater with ADVAIR DISKUS than with the use of either fluticasone propionate or salmeterol alone. In addition, clinical trials showed similar results between ADVAIR DISKUS and the concurrent use of fluticasone propionate plus salmeterol at corresponding doses from separate inhalers.

Studies Comparing ADVAIR DISKUS to Fluticasone Propionate Alone or Salmeterol Alone: Three (3) double-blind, parallel-group clinical trials were conducted with ADVAIR DISKUS in 1,208 adolescent and adult patients (≥12 years, baseline FEV1 63% to 72% of predicted normal) with asthma that was not optimally controlled on their current therapy. All treatments were inhalation powders given as 1 inhalation from the DISKUS device twice daily, and other maintenance therapies were discontinued.

Study 1: Clinical Trial With ADVAIR DISKUS 100/50: This placebo-controlled, 12-week, US study compared ADVAIR DISKUS 100/50 with its individual components, fluticasone propionate 100 mcg and salmeterol 50 mcg. The study was stratified according to baseline asthma maintenance therapy; patients were using either inhaled corticosteroids (N = 250) (daily doses of beclomethasone dipropionate 252 to 420 mcg; flunisolide 1,000 mcg; fluticasone propionate inhalation aerosol 176 mcg; or triamcinolone acetonide 600 to 1,000 mcg) or salmeterol (N = 106). Baseline FEV1 measurements were similar across treatments: ADVAIR DISKUS 100/50, 2.17 L; fluticasone propionate 100 mcg, 2.11 L; salmeterol, 2.13 L; and placebo, 2.15 L.

Predefined withdrawal criteria for lack of efficacy, an indicator of worsening asthma, were utilized for this placebo-controlled study. Worsening asthma was defined as a clinically important decrease in FEV1 or PEF, increase in use of VENTOLIN® (albuterol, USP) Inhalation Aerosol, increase in night awakenings due to asthma, emergency intervention or hospitalization due to asthma, or requirement for asthma medication not allowed by the protocol. As shown in Table 4, statistically significantly fewer patients receiving ADVAIR DISKUS 100/50 were withdrawn due to worsening asthma compared with fluticasone propionate, salmeterol, and placebo.

Table 4. Percent of Patients Withdrawn Due to Worsening Asthma in Patients Previously Treated With Either Inhaled Corticosteroids or Salmeterol (Study 1)
ADVAIR DISKUS; 100/50; (N = 87) | Fluticasone Propionate; 100 mcg; (N = 85) | Salmeterol; 50 mcg; (N = 86) | Placebo; (N = 77)
3% | 11% | 35% | 49%

The FEV1 results are displayed in Figure 2. Because this trial used predetermined criteria for worsening asthma, which caused more patients in the placebo group to be withdrawn, FEV1 results at Endpoint (last available FEV1 result) are also provided. Patients receiving ADVAIR DISKUS 100/50 had significantly greater improvements in FEV1 (0.51 L, 25%) compared with fluticasone propionate 100 mcg (0.28 L, 15%), salmeterol (0.11 L, 5%), and placebo (0.01 L, 1%). These improvements in FEV1 with ADVAIR DISKUS were achieved regardless of baseline asthma maintenance therapy (inhaled corticosteroids or salmeterol).

Figure 2. Mean Percent Change From Baseline in FEV1 in Patients With Asthma Previously Treated With Either Inhaled Corticosteroids or Salmeterol (Study 1)

The effect of ADVAIR DISKUS 100/50 on morning and evening PEF endpoints is shown in Table 5.

Table 5. Peak Expiratory Flow Results for Patients With Asthma Previously Treated With Either Inhaled Corticosteroids or Salmeterol (Study 1)
Efficacy Variablea | ADVAIR DISKUS 100/50; (N = 87) | Fluticasone Propionate; 100 mcg; (N = 85) | Salmeterol; 50 mcg; (N = 86) | Placebo; (N = 77)
AM PEF (L/min)
Baseline | 393 | 374 | 369 | 382
Change from baseline | 53 | 17 | -2 | -24
PM PEF (L/min)
Baseline | 418 | 390 | 396 | 398
Change from baseline | 35 | 18 | -7 | -13

aChange from baseline = change from baseline at Endpoint (last available data).

The subjective impact of asthma on patients’ perception of health was evaluated through use of an instrument called the Asthma Quality of Life Questionnaire (AQLQ) (based on a 7-point scale where 1 = maximum impairment and 7 = none). Patients receiving ADVAIR DISKUS 100/50 had clinically meaningful improvements in overall asthma-specific quality of life as defined by a difference between groups of ≥0.5 points in change from baseline AQLQ scores (difference in AQLQ score of 1.25 compared with placebo).

Study 2: Clinical Trial With ADVAIR DISKUS 250/50: This placebo-controlled, 12-week, US study compared ADVAIR DISKUS 250/50 with its individual components, fluticasone propionate 250 mcg and salmeterol 50 mcg, in 349 patients with asthma using inhaled corticosteroids (daily doses of beclomethasone dipropionate 462 to 672 mcg; flunisolide 1,250 to 2,000 mcg; fluticasone propionate inhalation aerosol 440 mcg; or triamcinolone acetonide 1,100 to 1,600 mcg). Baseline FEV1 measurements were similar across treatments: ADVAIR DISKUS 250/50, 2.23 L; fluticasone propionate 250 mcg, 2.12 L; salmeterol, 2.20 L; and placebo, 2.19 L.

Efficacy results in this study were similar to those observed in Study 1. Patients receiving ADVAIR DISKUS 250/50 had significantly greater improvements in FEV1 (0.48 L, 23%) compared with fluticasone propionate 250 mcg (0.25 L, 13%), salmeterol (0.05 L, 4%), and placebo (decrease of 0.11 L, decrease of 5%). Statistically significantly fewer patients receiving ADVAIR DISKUS 250/50 were withdrawn from this study for worsening asthma (4%) compared with fluticasone propionate (22%), salmeterol (38%), and placebo (62%). In addition, ADVAIR DISKUS 250/50 was superior to fluticasone propionate, salmeterol, and placebo for improvements in morning and evening PEF. Patients receiving ADVAIR DISKUS 250/50 also had clinically meaningful improvements in overall asthma-specific quality of life as described in Study 1 (difference in AQLQ score of 1.29 compared with placebo).

Study 3: Clinical Trial With ADVAIR DISKUS 500/50: This 28-week, non-US study compared ADVAIR DISKUS 500/50 with fluticasone propionate 500 mcg alone and concurrent therapy (salmeterol 50 mcg plus fluticasone propionate 500 mcg administered from separate inhalers) twice daily in 503 patients with asthma using inhaled corticosteroids (daily doses of beclomethasone dipropionate 1,260 to 1,680 mcg; budesonide 1,500 to 2,000 mcg; flunisolide 1,500 to 2,000 mcg; or fluticasone propionate inhalation aerosol 660 to 880 mcg [750 to 1,000 mcg inhalation powder]). The primary efficacy parameter, morning PEF, was collected daily for the first 12 weeks of the study. The primary purpose of weeks 13 to 28 was to collect safety data.

Baseline PEF measurements were similar across treatments: ADVAIR DISKUS 500/50, 359 L/min; fluticasone propionate 500 mcg, 351 L/min; and concurrent therapy, 345 L/min. Morning PEF improved significantly with ADVAIR DISKUS 500/50 compared with fluticasone propionate 500 mcg over the 12-week treatment period. Improvements in morning PEF observed with ADVAIR DISKUS 500/50 were similar to improvements observed with concurrent therapy.

Onset of Action and Progression of Improvement in Asthma Control: The onset of action and progression of improvement in asthma control were evaluated in the 2 placebo-controlled US trials. Following the first dose, the median time to onset of clinically significant bronchodilatation (≥15% improvement in FEV1) in most patients was seen within 30 to 60 minutes. Maximum improvement in FEV1 generally occurred within 3 hours, and clinically significant improvement was maintained for 12 hours (see Figure 3). Following the initial dose, predose FEV1 relative to Day 1 baseline improved markedly over the first week of treatment and continued to improve over the 12 weeks of treatment in both studies. No diminution in the 12-hour bronchodilator effect was observed with either ADVAIR DISKUS 100/50 (Figures 3 and 4) or ADVAIR DISKUS 250/50 as assessed by FEV1 following 12 weeks of therapy.

- First Treatment Day

Figure 3. Percent Change in Serial 12-hour FEV1 in Patients With Asthma Previously Using Either Inhaled Corticosteroids or Salmeterol (Study 1)

- Last Treatment Day (Week 12)

Figure 4. Percent Change in Serial 12-hour FEV1 in Patients With Asthma Previously Using Either Inhaled Corticosteroids or Salmeterol (Study 1)

Reduction in asthma symptoms, use of rescue VENTOLIN Inhalation Aerosol, and improvement in morning and evening PEF also occurred within the first day of treatment with ADVAIR DISKUS, and continued to improve over the 12 weeks of therapy in both studies.

Pediatric Patients: In a 12-week US study, ADVAIR DISKUS 100/50 twice daily was compared with fluticasone propionate inhalation powder 100 mcg twice daily in 203 children with asthma aged 4 to 11 years. At study entry, the children were symptomatic on low doses of inhaled corticosteroids (beclomethasone dipropionate 252 to 336 mcg/day; budesonide 200 to 400 mcg/day; flunisolide 1,000 mcg/day; triamcinolone acetonide 600 to 1,000 mcg/day; or fluticasone propionate 88 to 250 mcg/day). The primary objective of this study was to determine the safety of ADVAIR DISKUS 100/50 compared with fluticasone propionate inhalation powder 100 mcg in this age-group; however, the study also included secondary efficacy measures of pulmonary function. Morning predose FEV1 was obtained at baseline and Endpoint (last available FEV1 result) in children aged 6 to 11 years. In patients receiving ADVAIR DISKUS 100/50, FEV1 increased from 1.70 L at baseline (N = 79) to 1.88 L at Endpoint (N = 69) compared with an increase from 1.65 L at baseline (N = 83) to 1.77 L at Endpoint (N = 75) in patients receiving fluticasone propionate 100 mcg.

The findings of this study, along with extrapolation of efficacy data from patients aged 12 years and older, support the overall conclusion that ADVAIR DISKUS 100/50 is efficacious in the treatment of asthma in patients aged 4 to 11 years.

14.2 Chronic Obstructive Pulmonary Disease

The efficacy of ADVAIR DISKUS 250/50 and ADVAIR DISKUS 500/50 in the treatment of patients with COPD was evaluated in 6 randomized, double-blind, parallel-group clinical trials in adult patients aged 40 years and older. These trials were primarily designed to evaluate the efficacy of ADVAIR DISKUS on lung function (3 trials), exacerbations (2 trials), and survival (1 trial).

Lung Function: Two of the 3 clinical trials primarily designed to evaluate the efficacy of ADVAIR DISKUS on lung function were conducted in 1,414 patients with COPD associated with chronic bronchitis. In these 2 trials, all the patients had a history of cough productive of sputum that was not attributable to another disease process on most days for at least 3 months of the year for at least 2 years. The trials were randomized, double-blind, parallel-group, 24-week treatment duration. One trial evaluated the efficacy of ADVAIR DISKUS 250/50 compared with its components fluticasone propionate 250 mcg and salmeterol 50 mcg and with placebo, and the other trial evaluated the efficacy of ADVAIR DISKUS 500/50 compared with its components fluticasone propionate 500 mcg and salmeterol 50 mcg and with placebo. Study treatments were inhalation powders given as 1 inhalation from the DISKUS device twice daily. Maintenance COPD therapies were discontinued, with the exception of theophylline. The patients had a mean pre-bronchodilator FEV1 of 41% and 20% reversibility at study entry. Percent reversibility was calculated as 100 times (FEV1 post-albuterol minus FEV1 pre-albuterol)/FEV1 pre-albuterol.

Improvements in lung function (as defined by predose and postdose FEV1) were significantly greater with ADVAIR DISKUS than with fluticasone propionate, salmeterol, or placebo. The improvement in lung function with ADVAIR DISKUS 500/50 was similar to the improvement seen with ADVAIR DISKUS 250/50.

Figures 5 and 6 display predose and 2-hour postdose, respectively, FEV1 results for the study with ADVAIR DISKUS 250/50. To account for patient withdrawals during the study, FEV1 at Endpoint (last evaluable FEV1) was evaluated. Patients receiving ADVAIR DISKUS 250/50 had significantly greater improvements in predose FEV1 at Endpoint (165 mL, 17%) compared with salmeterol 50 mcg (91 mL, 9%) and placebo (1 mL, 1%), demonstrating the contribution of fluticasone propionate to the improvement in lung function with ADVAIR DISKUS (Figure 5). Patients receiving ADVAIR DISKUS 250/50 had significantly greater improvements in postdose FEV1 at Endpoint (281 mL, 27%) compared with fluticasone propionate 250 mcg (147 mL, 14%) and placebo (58 mL, 6%), demonstrating the contribution of salmeterol to the improvement in lung function with ADVAIR DISKUS (Figure 6).

Figure 5. Predose FEV1: Mean Percent Change From Baseline in Patients With Chronic Obstructive Pulmonary Disease

Figure 6. Two-Hour Postdose FEV1: Mean Percent Changes From Baseline Over Time in Patients With Chronic Obstructive Pulmonary Disease

The third trial was a 1-year study that evaluated ADVAIR DISKUS 500/50, fluticasone propionate 500 mcg, salmeterol 50 mcg, and placebo in 1,465 patients. The patients had an established history of COPD and exacerbations, a pre-bronchodilator FEV1 <70% of predicted at study entry, and 8.3% reversibility. The primary endpoint was the comparison of pre-bronchodilator FEV1 in the groups receiving ADVAIR DISKUS 500/50 or placebo. Patients treated with ADVAIR DISKUS 500/50 had greater improvements in FEV1 (113 mL, 10%) compared with fluticasone propionate 500 mcg (7 mL, 2%), salmeterol (15 mL, 2%), and placebo (-60 mL, -3%).

Exacerbations: Two studies were primarily designed to evaluate the effect of ADVAIR DISKUS 250/50 on exacerbations. In these 2 studies, exacerbations were defined as worsening of 2 or more major symptoms (dyspnea, sputum volume, and sputum purulence) or worsening of any 1 major symptom together with any 1 of the following minor symptoms: sore throat, colds (nasal discharge and/or nasal congestion), fever without other cause, and increased cough or wheeze for at least 2 consecutive days. COPD exacerbations were considered of moderate severity if treatment with systemic corticosteroids and/or antibiotics was required and were considered severe if hospitalization was required.

Exacerbations were also evaluated as a secondary outcome in the 1- and 3-year trials with ADVAIR DISKUS 500/50. There was not a symptomatic definition of exacerbation in these 2 trials. Exacerbations were defined in terms of severity requiring treatment with antibiotics and/or systemic corticosteroids (moderately severe) or requiring hospitalization (severe).

The 2 exacerbation trials with ADVAIR DISKUS 250/50 were identical studies designed to evaluate the effect of ADVAIR DISKUS 250/50 and salmeterol 50 mcg, each given twice daily, on exacerbations of COPD over a 12-month period. A total of 1,579 patients had an established history of COPD (but no other significant respiratory disorders). Patients had a pre-bronchodilator FEV1 of 33% of predicted, a mean reversibility of 23% at baseline, and a history of ≥1 COPD exacerbation in the previous year that was moderate or severe. All patients were treated with ADVAIR DISKUS 250/50 twice daily during a 4-week run-in period prior to being assigned study treatment with twice-daily ADVAIR DISKUS 250/50 or salmeterol 50 mcg. In both studies, treatment with ADVAIR DISKUS 250/50 resulted in a significantly lower annual rate of moderate/severe COPD exacerbations compared with salmeterol (30.5% reduction [95% CI: 17.0, 41.8], p<0.001) in the first study and (30.4% reduction [95% CI: 16.9, 41.7], p<0.001) in the second study. Patients treated with ADVAIR DISKUS 250/50 also had a significantly lower annual rate of exacerbations requiring treatment with oral corticosteroids compared with patients treated with salmeterol (39.7% reduction [95% CI: 22.8, 52.9], p <0.001) in the first study and (34.3% reduction [95% CI: 18.6, 47.0], p<0.001) in the second study. Secondary endpoints including pulmonary function and symptom scores improved more in patients treated with ADVAIR DISKUS 250/50 than with salmeterol 50 mcg in both studies

Exacerbations were evaluated in the 1- and the 3-year trials with ADVAIR DISKUS 500/50 as 1 of the secondary efficacy endpoints. In the 1-year trial, the group receiving ADVAIR DISKUS 500/50 had a significantly lower rate of moderate and severe exacerbations compared with placebo (25.4% reduction compared with placebo [95% CI: 13.5, 35.7]) but not when compared with its components (7.5% reduction compared with fluticasone propionate [95% CI: -7.3, 20.3] and 7% reduction compared with salmeterol [95% CI: -8.0, 19.9]). In the 3-year trial, the group receiving ADVAIR DISKUS 500/50 had a significantly lower rate of moderate and severe exacerbations compared with each of the other treatment groups (25.1% reduction compared with placebo [95% CI: 18.6, 31.1], 9.0% reduction compared with fluticasone propionate [95% CI: 1.2, 16.2], and 12.2% reduction compared with salmeterol [95% CI: 4.6, 19.2]).

There were no studies conducted to directly compare the efficacy of ADVAIR DISKUS 250/50 with ADVAIR DISKUS 500/50 on exacerbations. Across studies, the reduction in exacerbations seen with ADVAIR DISKUS 500/50 was not greater than the reduction in exacerbations seen with ADVAIR DISKUS 250/50.

Survival: A 3-year multicenter, international study evaluated the efficacy of ADVAIR DISKUS 500/50 compared with fluticasone propionate 500 mcg, salmeterol 50 mcg, and placebo on survival in 6,112 patients with COPD. During the study patients were permitted usual COPD therapy with the exception of other inhaled corticosteroids and long-acting bronchodilators. The patients were aged 40 to 80 years with an established history of COPD, a pre-bronchodilator FEV1 <60% of predicted at study entry, and <10% of predicted reversibility. Each patient who withdrew from double-blind treatment for any reason was followed for the full 3-year study period to determine survival status. The primary efficacy endpoint was all-cause mortality. Survival with ADVAIR DISKUS 500/50 was not significantly improved compared with placebo or the individual components (all-cause mortality rate 12.6% ADVAIR DISKUS versus 15.2% placebo). The rates for all-cause mortality were 13.5% and 16.0% in the groups treated with salmeterol 50 mcg and fluticasone propionate 500 mcg, respectively. Secondary outcomes, including pulmonary function (post-bronchodilator FEV1), improved with ADVAIR DISKUS 500/50, salmeterol, and fluticasone propionate 500/50 compared with placebo.

16 HOW SUPPLIED/STORAGE AND HANDLING

ADVAIR DISKUS 100/50 is supplied as a disposable purple device containing 60 blisters. The DISKUS inhalation device is packaged within a plastic-coated, moisture-protective foil pouch (NDC 33261-873-01).

ADVAIR DISKUS 250/50 is supplied as a disposable purple device containing 60 blisters. The DISKUS inhalation device is packaged within a plastic-coated, moisture-protective foil pouch (NDC 33261-874-01).

Store at controlled room temperature (see USP), 20° to 25°C (68° to 77°F), in a dry place away from direct heat or sunlight. Keep out of reach of children. The DISKUS inhalation device is not reusable. The device should be discarded 1 month after removal from the moisture-protective foil overwrap pouch or after all blisters have been used (when the dose indicator reads “0”), whichever comes first. Do not attempt to take the device apart.

17 PATIENT COUNSELING INFORMATION

See FDA-approved Medication Guide.

17.1 Asthma-Related Death

Patients with asthma should be informed that salmeterol, one of the active ingredients in ADVAIR DISKUS, increases the risk of asthma-related death and may increase the risk of asthma-related hospitalization in pediatric and adolescent patients. They should also be informed that currently available data are inadequate to determine whether concurrent use of inhaled corticosteroids or other long-term asthma control drugs mitigates the increased risk of asthma-related death from LABAs.

17.2 Not for Acute Symptoms

ADVAIR DISKUS is not meant to relieve acute asthma symptoms or exacerbations of COPD and extra doses should not be used for that purpose. Acute symptoms should be treated with an inhaled, short-acting beta2-agonist such as albuterol. The physician should provide the patient with such medication and instruct the patient in how it should be used.

Patients should be instructed to notify their physician immediately if they experience any of the following:

- Decreasing effectiveness of inhaled, short-acting beta2-agonists
- Need for more inhalations than usual of inhaled, short-acting beta2-agonists
- Significant decrease in lung function as outlined by the physician

Patients should not stop therapy with ADVAIR DISKUS without physician/provider guidance since symptoms may recur after discontinuation.

17.3 Do Not Use Additional Long-Acting Beta2-Agonists

When patients are prescribed ADVAIR DISKUS, other LABAs for asthma and COPD should not be used.

17.4 Risks Associated With Corticosteroid Therapy

Local Effects: Patients should be advised that localized infections with Candida albicans occurred in the mouth and pharynx in some patients. If oropharyngeal candidiasis develops, it should be treated with appropriate local or systemic (i.e., oral) antifungal therapy while still continuing therapy with ADVAIR DISKUS, but at times therapy with ADVAIR DISKUS may need to be temporarily interrupted under close medical supervision. Rinsing the mouth after inhalation is advised.

Pneumonia: Patients with COPD have a higher risk of pneumonia and should be instructed to contact their healthcare provider if they develop symptoms of pneumonia.

Immunosuppression: Patients who are on immunosuppressant doses of corticosteroids should be warned to avoid exposure to chickenpox or measles and, if exposed, to consult their physician without delay. Patients should be informed of potential worsening of existing tuberculosis, fungal, bacterial, viral, or parasitic infections, or ocular herpes simplex.

Hypercorticism and Adrenal Suppression: Patients should be advised that ADVAIR DISKUS may cause systemic corticosteroid effects of hypercorticism and adrenal suppression. Additionally, patients should be instructed that deaths due to adrenal insufficiency have occurred during and after transfer from systemic corticosteroids. Patients should taper slowly from systemic corticosteroids if transferring to ADVAIR DISKUS.

Reduction in Bone Mineral Density: Patients who are at an increased risk for decreased BMD should be advised that the use of corticosteroids may pose an additional risk.

Reduced Growth Velocity: Patients should be informed that orally inhaled corticosteroids, including fluticasone propionate, a component of ADVAIR DISKUS, may cause a reduction in growth velocity when administered to pediatric patients. Physicians should closely follow the growth of children and adolescents taking corticosteroids by any route.

Ocular Effects: Long-term use of inhaled corticosteroids may increase the risk of some eye problems (cataracts or glaucoma); regular eye examinations should be considered.

17.5 Risks Associated With Beta-Agonist Therapy

Patients should be informed of adverse effects associated with beta2-agonists, such as palpitations, chest pain, rapid heart rate, tremor, or nervousness.

ADVAIR, ADVAIR DISKUS, DISKHALER, DISKUS, FLONASE, FLOVENT, ROTADISK, SEREVENT, and VENTOLIN are registered trademarks of GlaxoSmithKline.

GlaxoSmithKline

Research Triangle Park, NC 27709

©2011, GlaxoSmithKline. All rights reserved.

September 2011

ADD: 9PI

MEDICATION GUIDE

ADVAIR [ad′ vair] DISKUS® 100/50

(fluticasone propionate 100 mcg and salmeterol 50 mcg inhalation powder)

ADVAIR DISKUS® 250/50

(fluticasone propionate 250 mcg and salmeterol 50 mcg inhalation powder)

ADVAIR DISKUS® 500/50

(fluticasone propionate 500 mcg and salmeterol 50 mcg inhalation powder)

Read the Medication Guide that comes with ADVAIR DISKUS before you start using it and each time you get a refill. There may be new information. This Medication Guide does not take the place of talking to your healthcare provider about your medical condition or treatment.

What is the most important information I should know about ADVAIR DISKUS?

ADVAIR DISKUS can cause serious side effects, including:

- People with asthma who take long-acting beta2-adrenergic agonist (LABA) medicines, such as salmeterol (one of the medicines in ADVAIR DISKUS), have an increased risk of death from asthma problems. It is not known whether fluticasone propionate, the other medicine in ADVAIR DISKUS, reduces the risk of death from asthma problems seen with salmeterol.
  - Call your healthcare provider if breathing problems worsen over time while using ADVAIR DISKUS. You may need different treatment.
  - Get emergency medical care if:
    - breathing problems worsen quickly and
    - you use your rescue inhaler medicine, but it does not relieve your breathing problems.
- ADVAIR DISKUS should be used only if your healthcare provider decides that your asthma is not well controlled with a long-term asthma control medicine, such as inhaled corticosteroids.
- When your asthma is well controlled, your healthcare provider may tell you to stop taking ADVAIR DISKUS. Your healthcare provider will decide if you can stop ADVAIR DISKUS without loss of asthma control. Your healthcare provider may prescribe a different asthma control medicine for you, such as an inhaled corticosteroid.
- Children and adolescents who take LABA medicines may have an increased risk of being hospitalized for asthma problems.

What is ADVAIR DISKUS?

- ADVAIR DISKUS combines an inhaled corticosteroid medicine, fluticasone propionate (the same medicine found in FLOVENT®), and a LABA medicine, salmeterol (the same medicine found in SEREVENT®).
  - Inhaled corticosteroids help to decrease inflammation in the lungs. Inflammation in the lungs can lead to asthma symptoms.
  - LABA medicines are used in people with asthma and chronic obstructive pulmonary disease (COPD). LABA medicines help the muscles around the airways in your lungs stay relaxed to prevent symptoms, such as wheezing and shortness of breath. These symptoms can happen when the muscles around the airways tighten. This makes it hard to breathe. In severe cases, wheezing can stop your breathing and cause death if not treated right away.
- ADVAIR DISKUS is used for asthma and COPD as follows:

Asthma:

ADVAIR DISKUS is used to control symptoms of asthma and to prevent symptoms such as wheezing in adults and children aged 4 years and older.

ADVAIR DISKUS contains salmeterol (the same medicine found in SEREVENT). LABA medicines, such as salmeterol, increase the risk of death from asthma problems.

ADVAIR DISKUS is not for adults and children with asthma who are well controlled with an asthma control medicine, such as a low to medium dose of an inhaled corticosteroid medicine.

COPD:

COPD is a chronic lung disease that includes chronic bronchitis, emphysema, or both. ADVAIR DISKUS 250/50 is used long term, 2 times each day to help improve lung function for better breathing in adults with COPD. ADVAIR DISKUS 250/50 has been shown to decrease the number of flare-ups and worsening of COPD symptoms (exacerbations).

Who should not use ADVAIR DISKUS?

Do not use ADVAIR DISKUS:

- to treat sudden, severe symptoms of asthma or COPD and
- if you have a severe allergy to milk proteins. Ask your doctor if you are not sure.

What should I tell my healthcare provider before using ADVAIR DISKUS?

Tell your healthcare provider about all of your health conditions, including if you:

- have heart problems
- have high blood pressure
- have seizures
- have thyroid problems
- have diabetes
- have liver problems
- have osteoporosis
- have an immune system problem
- are pregnant or planning to become pregnant. It is not known if ADVAIR DISKUS may harm your unborn baby.
- are breastfeeding. It is not known if ADVAIR DISKUS passes into your milk and if it can harm your baby.
- are allergic to any of the ingredients in ADVAIR DISKUS, any other medicines, or food products. See the end of this Medication Guide for a complete list of the ingredients in ADVAIR DISKUS.
- are exposed to chickenpox or measles

Tell your healthcare provider about all the medicines you take including prescription and non-prescription medicines, vitamins, and herbal supplements. ADVAIR DISKUS and certain other medicines may interact with each other. This may cause serious side effects. Especially, tell your healthcare provider if you take ritonavir. The anti-HIV medicines NORVIR® (ritonavir capsules) Soft Gelatin, NORVIR (ritonavir oral solution), and KALETRA® (lopinavir/ritonavir) Tablets contain ritonavir.

Know the medicines you take. Keep a list and show it to your healthcare provider and pharmacist each time you get a new medicine.

How do I use ADVAIR DISKUS?

See the step-by-step instructions for using ADVAIR DISKUS at the end of this Medication Guide. Do not use ADVAIR DISKUS unless your healthcare provider has taught you and you understand everything. Ask your healthcare provider or pharmacist if you have any questions.

- Children should use ADVAIR DISKUS with an adult’s help, as instructed by the child’s healthcare provider.
- Use ADVAIR DISKUS exactly as prescribed. Do not use ADVAIR DISKUS more often than prescribed. ADVAIR DISKUS comes in 3 strengths. Your healthcare provider has prescribed the one that is best for your condition.
- The usual dosage of ADVAIR DISKUS is 1 inhalation 2 times each day (morning and evening). The 2 doses should be about 12 hours apart. Rinse your mouth with water after using ADVAIR DISKUS.
- If you take more ADVAIR DISKUS than your doctor has prescribed, get medical help right away if you have any unusual symptoms, such as worsening shortness of breath, chest pain, increased heart rate, or shakiness.
- If you miss a dose of ADVAIR DISKUS, just skip that dose. Take your next dose at your usual time. Do not take 2 doses at one time.
- Do not use a spacer device with ADVAIR DISKUS.
- Do not breathe into ADVAIR DISKUS.
- While you are using ADVAIR DISKUS 2 times each day, do not use other medicines that contain a LABA for any reason. Ask your healthcare provider or pharmacist if any of your other medicines are LABA medicines.
- Do not stop using ADVAIR DISKUS or other asthma medicines unless told to do so by your healthcare provider because your symptoms might get worse. Your healthcare provider will change your medicines as needed.
- ADVAIR DISKUS does not relieve sudden symptoms. Always have a rescue inhaler medicine with you to treat sudden symptoms. If you do not have an inhaled, short-acting bronchodilator, call your healthcare provider to have one prescribed for you.
- Call your healthcare provider or get medical care right away if:
  - your breathing problems worsen with ADVAIR DISKUS
  - you need to use your rescue inhaler medicine more often than usual
  - your rescue inhaler medicine does not work as well for you at relieving symptoms
  - you need to use 4 or more inhalations of your rescue inhaler medicine for 2 or more days in a row
  - you use 1 whole canister of your rescue inhaler medicine in 8 weeks’ time
  - your peak flow meter results decrease. Your healthcare provider will tell you the numbers that are right for you.
  - you have asthma and your symptoms do not improve after using ADVAIR DISKUS regularly for 1 week

What are the possible side effects with ADVAIR DISKUS?

ADVAIR DISKUS can cause serious side effects, including:

- See “What is the most important information I should know about ADVAIR DISKUS?”
- serious allergic reactions. Call your healthcare provider or get emergency medical care if you get any of the following symptoms of a serious allergic reaction:
  - rash
  - hives
  - swelling of the face, mouth, and tongue
  - breathing problems
- sudden breathing problems immediately after inhaling your medicine
- effects on heart
  - increased blood pressure
  - a fast and irregular heartbeat
  - chest pain
- effects on nervous system
  - tremor
  - nervousness
- reduced adrenal function (may result in loss of energy)
- changes in blood (sugar, potassium, certain types of white blood cells)
- weakened immune system and a higher chance of infections
- lower bone mineral density. This may be a problem for people who already have a higher chance of low bone density (osteoporosis).
- eye problems including glaucoma and cataracts. You should have regular eye exams while using ADVAIR DISKUS.
- slowed growth in children. A child’s growth should be checked often.
- pneumonia. People with COPD have a higher chance of getting pneumonia. ADVAIR DISKUS may increase the chance of getting pneumonia. Call your healthcare provider if you notice any of the following symptoms:
  - increase in mucus (sputum) production
  - change in mucus color
  - fever
  - chills
  - increased cough
  - increased breathing problems

Common side effects of ADVAIR DISKUS include:

Asthma:

- upper respiratory tract infection
- throat irritation
- hoarseness and voice changes
- thrush in the mouth and throat
- bronchitis
- cough
- headache
- nausea and vomiting

In children with asthma, infections in the ear, nose, and throat are common.

COPD:

- thrush in the mouth and throat
- throat irritation
- hoarseness and voice changes
- viral respiratory infections
- headache
- muscle and bone pain

Tell your healthcare provider about any side effect that bothers you or that does not go away.

These are not all the side effects with ADVAIR DISKUS. Ask your healthcare provider or pharmacist for more information.

Call your doctor for medical advice about side effects. You may report side effects to FDA at 1-800-FDA-1088.

How do I store ADVAIR DISKUS?

- Store ADVAIR DISKUS at room temperature between 68°F to 77°F (20°C to 25°C). Keep in a dry place away from heat and sunlight.
- Safely discard ADVAIR DISKUS 1 month after you remove it from the foil pouch, or after the dose indicator reads “0”, whichever comes first.
- Keep ADVAIR DISKUS and all medicines out of the reach of children.

General Information about ADVAIR DISKUS

Medicines are sometimes prescribed for purposes not mentioned in a Medication Guide. Do not use ADVAIR DISKUS for a condition for which it was not prescribed. Do not give your ADVAIR DISKUS to other people, even if they have the same condition that you have. It may harm them.

This Medication Guide summarizes the most important information about ADVAIR DISKUS. If you would like more information, talk with your healthcare provider or pharmacist. You can ask your healthcare provider or pharmacist for information about ADVAIR DISKUS that was written for healthcare professionals. You can also contact the company that makes ADVAIR DISKUS (toll free) at 1-888-825-5249 or at www.advair.com.

What are the ingredients in ADVAIR DISKUS?

Active ingredients: fluticasone propionate, salmeterol xinafoate

Inactive ingredient: lactose (contains milk proteins)

Instructions for Using ADVAIR DISKUS

Follow the instructions below for using your ADVAIR DISKUS. You will breathe in (inhale) the medicine from the DISKUS®. If you have any questions, ask your healthcare provider or pharmacist.

Take ADVAIR DISKUS out of the box and foil pouch. Write the “Pouch opened” and “Use by” dates on the label on top of the DISKUS. The “Use by” date is 1 month from date of opening the pouch.

- The DISKUS will be in the closed position when the pouch is opened.
- The dose indicator on the top of the DISKUS tells you how many doses are left. The dose indicator number will decrease each time you use the DISKUS. After you have used 55 doses from the DISKUS, the numbers 5 to 0 will appear in red to warn you that there are only a few doses left (see Figure 1). If you are using a “sample” DISKUS, the numbers 5 to 0 will appear in red after 9 doses.

Figure 1

Taking a dose from the DISKUS requires the following 3 simple steps: Open, Click, Inhale.

1. OPEN

Hold the DISKUS in one hand and put the thumb of your other hand on the thumbgrip. Push your thumb away from you as far as it will go until the mouthpiece appears and snaps into position (see Figure 2).

Figure 2

2. CLICK

Hold the DISKUS in a level, flat position with the mouthpiece towards you. Slide the lever away from you as far as it will go until it clicks (see Figure 3). The DISKUS is now ready to use.

Figure 3

Every time the lever is pushed back, a dose is ready to be inhaled. This is shown by a decrease in numbers on the dose counter. To avoid releasing or wasting doses once the DISKUS is ready:

- Do not close the DISKUS.
- Do not tilt the DISKUS.
- Do not play with the lever.
- Do not move the lever more than once.

3. INHALE

Before inhaling your dose from the DISKUS, breathe out (exhale) fully while holding the DISKUS level and away from your mouth (see Figure 4). Remember, never breathe out into the DISKUS mouthpiece.

Figure 4

Put the mouthpiece to your lips (see Figure 5). Breathe in quickly and deeply through the DISKUS. Do not breathe in through your nose.

Figure 5

Remove the DISKUS from your mouth. Hold your breath for about 10 seconds, or for as long as is comfortable. Breathe out slowly.

The DISKUS delivers your dose of medicine as a very fine powder. Patients may or may not taste or feel the powder. Do not use an extra dose from the DISKUS if you do not feel or taste the medicine.

Rinse your mouth with water after breathing-in the medicine. Spit the water out. Do not swallow.

4. Close the DISKUS when you are finished taking a dose so that the DISKUS will be ready for you to take your next dose. Put your thumb on the thumbgrip and slide the thumbgrip back towards you as far as it will go (see Figure 6). The DISKUS will click shut. The lever will automatically return to its original position. The DISKUS is now ready for you to take your next scheduled dose, due in about 12 hours. (Repeat steps 1 to 4.)

Figure 6

Remember:

- Never breathe into the DISKUS.
- Never take the DISKUS apart.
- Always ready and use the DISKUS in a level, flat position.
- Do not use the DISKUS with a spacer device.
- After each dose, rinse your mouth with water and spit the water out. Do not swallow.
- Never wash the mouthpiece or any part of the DISKUS. Keep it dry.
- Always keep the DISKUS in a dry place.
- Never take an extra dose, even if you did not taste or feel the medicine.

This Medication Guide has been approved by the U.S. Food and Drug Administration.

ADVAIR DISKUS, DISKUS, FLOVENT, and SEREVENT are registered trademarks of GlaxoSmithKline.

The other brands listed are trademarks of their respective owners and are not trademarks of GlaxoSmithKline. The makers of these brands are not affiliated with and do not endorse GlaxoSmithKline or its products.

GlaxoSmithKline

Research Triangle Park, NC 27709

©2011, GlaxoSmithKline. All rights reserved.

January 2011

ADD:7MG

Repackaged By :
Aidarex Pharmaceuticals LLC,
Corona, CA 92880

PACKAGE LABEL

Principal Display Panel

NDC 33261-0873-01

ADVAIR DISKUS®

100/50

(fluticasone propionate 100 mcg and salmeterol* 50 mcg inhalation powder)

FOR ORAL INHALATION ONLY

Rx only

* Each blister contains 100 mcg of fluticasone propionate and 72.5 mcg of salmeterol xinafoate, equivalent to 50 mcg of salmeterol base, with lactose.

IMPORTANT: Read the accompanying Medication Guide leaflet carefully for further information.

Discard the Diskus® 1 month after removal from the overwrap. Fill in the dates on the Diskus® appropriately.

Dosage: Use only as directed by your doctor.

Store at controlled room temperature (see USP), 20o to 25oC (68o to 77oF) in a dry place away from direct heat or sunlight.

1 Diskus® Inhalation Device Containing 1 Foil Strip of 60 Blisters

GlaxoSmithKline

Research Triangle Park, NC 27709

Repackaged By :
Aidarex Pharmaceuticals LLC,
Corona, CA 92880

10000000046630 Rev. 9/07

PACKAGE LABEL

Principal Display Panel

NDC 33261-0874-01

ADVAIR DISKUS®

250/50

(fluticasone propionate 250 mcg and salmeterol* 50 mcg inhalation powder)

FOR ORAL INHALATION ONLY

Rx only

* Each blister contains 250 mcg of fluticasone propionate and 72.5 mcg of salmeterol xinafoate, equivalent to 50 mcg of salmeterol base, with lactose.

IMPORTANT: Read the accompanying Medication Guide leaflet carefully for further information.

Discard the Diskus® 1 month after removal from the overwrap. Fill in the dates on the Diskus® appropriately.

Dosage: Use only as directed by your doctor.

Store at controlled room temperature (see USP), 20o to 25oC (68o to 77oF) in a dry place away from direct heat or sunlight.

1 Diskus® Inhalation Device Containing 1 Foil Strip of 60 Blisters

GlaxoSmithKline

Research Triangle Park, NC 27709

Repackaged By :
Aidarex Pharmaceuticals LLC,
Corona, CA 92880

10000000046633 Rev. 10/07